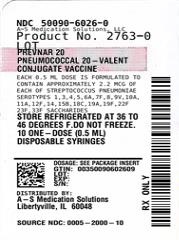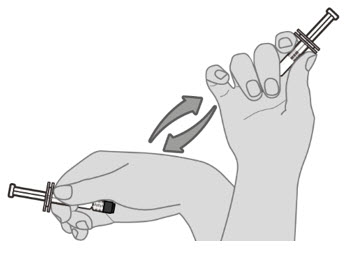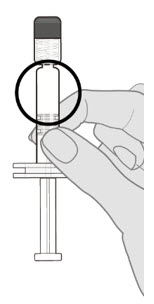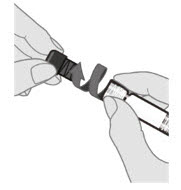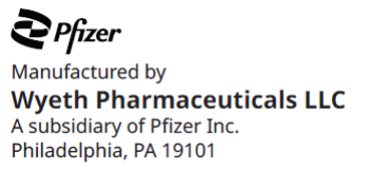 DRUG LABEL: PREVNAR 20
NDC: 50090-6026 | Form: INJECTION, SUSPENSION
Manufacturer: A-S Medication Solutions
Category: other | Type: VACCINE LABEL
Date: 20250813

ACTIVE INGREDIENTS: STREPTOCOCCUS PNEUMONIAE TYPE 1 CAPSULAR POLYSACCHARIDE DIPHTHERIA CRM197 PROTEIN CONJUGATE ANTIGEN 2.2 ug/0.5 mL; STREPTOCOCCUS PNEUMONIAE TYPE 3 CAPSULAR POLYSACCHARIDE DIPHTHERIA CRM197 PROTEIN CONJUGATE ANTIGEN 2.2 ug/0.5 mL; STREPTOCOCCUS PNEUMONIAE TYPE 4 CAPSULAR POLYSACCHARIDE DIPHTHERIA CRM197 PROTEIN CONJUGATE ANTIGEN 2.2 ug/0.5 mL; STREPTOCOCCUS PNEUMONIAE TYPE 5 CAPSULAR POLYSACCHARIDE DIPHTHERIA CRM197 PROTEIN CONJUGATE ANTIGEN 2.2 ug/0.5 mL; STREPTOCOCCUS PNEUMONIAE TYPE 6A CAPSULAR POLYSACCHARIDE DIPHTHERIA CRM197 PROTEIN CONJUGATE ANTIGEN 2.2 ug/0.5 mL; STREPTOCOCCUS PNEUMONIAE TYPE 6B CAPSULAR POLYSACCHARIDE DIPHTHERIA CRM197 PROTEIN CONJUGATE ANTIGEN 4.4 ug/0.5 mL; STREPTOCOCCUS PNEUMONIAE TYPE 7F CAPSULAR POLYSACCHARIDE DIPHTHERIA CRM197 PROTEIN CONJUGATE ANTIGEN 2.2 ug/0.5 mL; STREPTOCOCCUS PNEUMONIAE TYPE 8 CAPSULAR POLYSACCHARIDE DIPHTHERIA CRM197 PROTEIN CONJUGATE ANTIGEN 2.2 ug/0.5 mL; STREPTOCOCCUS PNEUMONIAE TYPE 9V CAPSULAR POLYSACCHARIDE DIPHTHERIA CRM197 PROTEIN CONJUGATE ANTIGEN 2.2 ug/0.5 mL; STREPTOCOCCUS PNEUMONIAE TYPE 10A CAPSULAR POLYSACCHARIDE DIPHTHERIA CRM197 PROTEIN CONJUGATE ANTIGEN 2.2 ug/0.5 mL; STREPTOCOCCUS PNEUMONIAE TYPE 11A CAPSULAR POLYSACCHARIDE DIPHTHERIA CRM197 PROTEIN CONJUGATE ANTIGEN 2.2 ug/0.5 mL; STREPTOCOCCUS PNEUMONIAE TYPE 12F CAPSULAR POLYSACCHARIDE DIPHTHERIA CRM197 PROTEIN CONJUGATE ANTIGEN 2.2 ug/0.5 mL; STREPTOCOCCUS PNEUMONIAE TYPE 14 CAPSULAR POLYSACCHARIDE DIPHTHERIA CRM197 PROTEIN CONJUGATE ANTIGEN 2.2 ug/0.5 mL; STREPTOCOCCUS PNEUMONIAE TYPE 15B CAPSULAR POLYSACCHARIDE DIPHTHERIA CRM197 PROTEIN CONJUGATE ANTIGEN 2.2 ug/0.5 mL; STREPTOCOCCUS PNEUMONIAE TYPE 18C CAPSULAR POLYSACCHARIDE DIPHTHERIA CRM197 PROTEIN CONJUGATE ANTIGEN 2.2 ug/0.5 mL; STREPTOCOCCUS PNEUMONIAE TYPE 19A CAPSULAR POLYSACCHARIDE DIPHTHERIA CRM197 PROTEIN CONJUGATE ANTIGEN 2.2 ug/0.5 mL; STREPTOCOCCUS PNEUMONIAE TYPE 19F CAPSULAR POLYSACCHARIDE DIPHTHERIA CRM197 PROTEIN CONJUGATE ANTIGEN 2.2 ug/0.5 mL; STREPTOCOCCUS PNEUMONIAE TYPE 22F CAPSULAR POLYSACCHARIDE DIPHTHERIA CRM197 PROTEIN CONJUGATE ANTIGEN 2.2 ug/0.5 mL; STREPTOCOCCUS PNEUMONIAE TYPE 23F CAPSULAR POLYSACCHARIDE DIPHTHERIA CRM197 PROTEIN CONJUGATE ANTIGEN 2.2 ug/0.5 mL; STREPTOCOCCUS PNEUMONIAE TYPE 33F CAPSULAR POLYSACCHARIDE DIPHTHERIA CRM197 PROTEIN CONJUGATE ANTIGEN 2.2 ug/0.5 mL
INACTIVE INGREDIENTS: PEG-20 SORBITAN OLEATE 100 ug/0.5 mL; ALUMINUM PHOSPHATE 125 ug/0.5 mL; CORYNEBACTERIUM DIPHTHERIAE CRM197 PROTEIN 51 ug/0.5 mL; SUCCINATE DIANION 295 ug/0.5 mL; SODIUM CHLORIDE 4.4 mg/0.5 mL

HIGHLIGHTS OF PRESCRIBING INFORMATION

These highlights do not include all the information needed to use PREVNAR 20 safely and effectively. See full prescribing information for PREVNAR 20.
PREVNAR 20® (Pneumococcal 20-valent Conjugate Vaccine), suspension for intramuscular injection
Initial U.S. Approval: 2021

RECENT MAJOR CHANGES

Indications and Usage | 04/2023
Dosage and Administration (2.2, 2.3, 2.4, 2.5, 2.6) | 04/2023
Warnings and Precautions, Apnea in Premature Infants (5.3) | 04/2023

1 INDICATIONS AND USAGE

Prevnar 20 is a vaccine indicated for

- active immunization for the prevention of invasive disease caused by Streptococcus pneumoniae serotypes 1, 3, 4, 5, 6A, 6B, 7F, 8, 9V, 10A, 11A, 12F, 14, 15B, 18C, 19A, 19F, 22F, 23F, and 33F in individuals 6 weeks of age and older. (1)
- active immunization for the prevention of otitis media caused by S. pneumoniae serotypes 4, 6B, 9V, 14, 18C, 19F, and 23F in individuals 6 weeks through 5 years of age. (1)
- active immunization for the prevention of pneumonia caused by S. pneumoniae serotypes 1, 3, 4, 5, 6A, 6B, 7F, 8, 9V, 10A, 11A, 12F, 14, 15B, 18C, 19A, 19F, 22F, 23F, and 33F in individuals 18 years of age and older. (1)

The indication for the prevention of pneumonia caused by S. pneumoniae serotypes 8, 10A, 11A, 12F, 15B, 22F, and 33F in individuals 18 years of age and older is approved under accelerated approval based on immune responses as measured by opsonophagocytic activity (OPA) assay. Continued approval for this indication may be contingent upon verification and description of clinical benefit in a confirmatory trial. (1)

2 DOSAGE AND ADMINISTRATION

For intramuscular administration only.

Children: Administer Prevnar 20 as a 4-dose immunization series at 2, 4, 6, and 12 through 15 months of age. (2.3)

Adults: Administer Prevnar 20 as a single dose in adults 18 years of age and older. (2.6)

3 DOSAGE FORMS AND STRENGTHS

0.5 mL suspension for intramuscular injection, supplied in a single-dose pre-filled syringe. (3)

4 CONTRAINDICATIONS

Severe allergic reaction (e.g., anaphylaxis) to any component of Prevnar 20 or to diphtheria toxoid. (4)

5 WARNINGS AND PRECAUTIONS

Apnea following intramuscular vaccination has been observed in some infants born prematurely. Decisions about when to administer Prevnar 20 to infants born prematurely should be based on consideration of the individual infant’s medical status, and the potential benefits and possible risks of vaccination. (5.3)

6 ADVERSE REACTIONS

- In individuals 2, 4, 6, and 12 through 15 months of age vaccinated with a 4‑dose schedule, the most commonly reported solicited adverse reactions >10% were irritability (>60%), pain at the injection site (>30%), drowsiness (>30%), decreased appetite and injection site redness (>20%), injection site swelling (>10%), and fever (>10%). (6.1)
- In individuals 15 months through 17 years of age vaccinated with a single dose, the most commonly reported solicited adverse reactions >10% were irritability (>60% in individuals less than 2 years of age), pain at the injection site (>50%), drowsiness (>40% in individuals less than 2 years of age), fatigue and muscle pain (>20% in individuals 2 years of age and older), decreased appetite (>20% in individuals less than 2 years of age), injection site swelling and injection site redness (>10%) and headache (>10% in individuals 5 years of age and older), and fever (>10% in individuals less than 2 years of age). (6.1)
- In individuals 18 through 59 years of age, the most commonly reported solicited adverse reactions >10% were pain at the injection site (>70%), muscle pain (>50%), fatigue (>40%), headache (>30%), and arthralgia and injection site swelling (>10%). (6.1)
- In individuals 60 years of age and older, the most commonly reported solicited adverse reactions >10% were pain at the injection site (>50%), muscle pain and fatigue (>30%), headache (>20%), and arthralgia (>10%). (6.1)

To report SUSPECTED ADVERSE REACTIONS, contact Pfizer Inc. at 1-800-438-1985 or VAERS at 1-800-822-7967 or http://vaers.hhs.gov.

FULL PRESCRIBING INFORMATION

1 INDICATIONS AND USAGE

Prevnar 20® is a vaccine indicated for

- active immunization for the prevention of invasive disease caused by Streptococcus pneumoniae serotypes 1, 3, 4, 5, 6A, 6B, 7F, 8, 9V, 10A, 11A, 12F, 14, 15B, 18C, 19A, 19F, 22F, 23F, and 33F in individuals 6 weeks of age and older.
- active immunization for the prevention of otitis media caused by S. pneumoniae serotypes 4, 6B, 9V, 14, 18C, 19F, and 23F in individuals 6 weeks through 5 years of age.
- active immunization for the prevention of pneumonia caused by S. pneumoniae serotypes 1, 3, 4, 5, 6A, 6B, 7F, 8, 9V, 10A, 11A, 12F, 14, 15B, 18C, 19A, 19F, 22F, 23F, and 33F in individuals 18 years of age and older.

The indication for the prevention of pneumonia caused by S. pneumoniae serotypes 8, 10A, 11A, 12F, 15B, 22F, and 33F in individuals 18 years of age and older is approved under accelerated approval based on immune responses as measured by opsonophagocytic activity (OPA) assay [see Clinical Studies (14.2)]. Continued approval for this indication may be contingent upon verification and description of clinical benefit in a confirmatory trial.

2 DOSAGE AND ADMINISTRATION

For intramuscular administration only.

2.1 Preparation

Do not mix Prevnar 20 with other vaccines/products in the same syringe.

Step 1. Resuspend drug product
Hold the pre-filled syringe horizontally between the thumb and the forefinger and shake vigorously until the vaccine is a homogeneous white suspension. Do not use the vaccine if it cannot be re-suspended.

Step 2. Visual inspection
Visually inspect the vaccine for large particulate matter and discoloration prior to administration. Do not use if large particulate matter or discoloration is found. If the vaccine is not a homogeneous suspension, repeat Steps 1 and 2.

Step 3. Remove syringe cap
Remove the syringe cap by slowly turning the cap counterclockwise while holding the Luer lock adapter.
Avoid pressing the syringe plunger rod while removing the syringe cap.

Step 4. Attach a sterile needle
Hold the Luer lock adapter and attach a needle appropriate for intramuscular administration to the pre-filled syringe by turning clockwise.

2.2 Administration

For intramuscular injection only.

Each 0.5-mL dose is to be injected intramuscularly using a sterile needle attached to the supplied pre-filled syringe.

2.3 Vaccination Schedule for Individuals 6 Weeks Through 15 Months of Age

Administer Prevnar 20 as a 4-dose series at 2, 4, 6, and 12 through 15 months of age (and at least 2 months after the third dose). The first dose may be given as early as 6 weeks of age.

2.4 Catch-Up Vaccination Schedule for Unvaccinated Individuals 7 Months Through 17 Years of Age

Individuals 7 months through 17 years of age who have never received a pneumococcal conjugate vaccine may receive Prevnar 20 according to the schedule in Table 1:

Table 1. Catch-Up Vaccination Schedule for Individuals Initiating Vaccination at 7 Months Through 17 Years of Age [The vaccination schedule is based on the catch-up schedule for Prevnar 13 (Pneumococcal 13-valent Conjugate Vaccine [Diphtheria CRM197 Protein]).]
Age at First Dose | Total Number of 0.5-mL Doses
7 through 11 months of age | 3 [The first 2 doses at least 4 weeks apart; third dose after the one-year birthday, separated from the second dose by at least 2 months.]
12 through 23 months of age | 2 [Two doses at least 2 months apart.]
24 months of age and above | 1

2.5 Catch-Up Vaccination Schedule for Individuals Previously Vaccinated With One or More Doses of a Lower Valency Pneumococcal Conjugate Vaccine

Administer a single dose of Prevnar 20 to individuals 15 months through 17 years of age previously vaccinated with one or more doses of a lower valency pneumococcal conjugate vaccine. The dose of Prevnar 20 should be administered at least 8 weeks after the last dose of the lower valency pneumococcal conjugate vaccine.

2.6 Vaccination Schedule for Individuals 18 Years of Age and Older

Prevnar 20 is administered as a single dose.

3 DOSAGE FORMS AND STRENGTHS

Prevnar 20 is a suspension for intramuscular injection available in a 0.5 mL single-dose pre-filled syringe.

4 CONTRAINDICATIONS

Do not administer Prevnar 20 to individuals with a severe allergic reaction (e.g., anaphylaxis) to any component of Prevnar 20 or to diphtheria toxoid [see Description (11)].

5 WARNINGS AND PRECAUTIONS

5.1 Management of Acute Allergic Reactions

Appropriate medical treatment and supervision used to manage immediate allergic reactions must be immediately available should an acute anaphylactic reaction occur following administration of Prevnar 20.

5.2 Altered Immunocompetence

Safety and immunogenicity data on Prevnar 20 are not available for individuals in immunocompromised groups and vaccination should be considered on an individual basis.

Based on experience with pneumococcal vaccines, individuals with altered immunocompetence may have reduced immune responses to Prevnar 20.

5.3 Apnea in Premature Infants

Apnea following intramuscular vaccination has been observed in some infants born prematurely. Decisions about when to administer Prevnar 20 to infants born prematurely should be based on consideration of the individual infant’s medical status and the potential benefits and possible risks of vaccination.

6 ADVERSE REACTIONS

6.1 Clinical Trials Experience

Because clinical trials are conducted under widely varying conditions, adverse reaction rates observed in the clinical trials of a vaccine cannot be directly compared to rates in the clinical trials of another vaccine and may not reflect the rates observed in practice.

In individuals 2, 4, 6, and 12 through 15 months of age vaccinated with a 4-dose schedule, the most commonly reported solicited adverse reactions >10% were irritability (>60%), pain at the injection site (>30%), drowsiness (>30%), decreased appetite and injection site redness (>20%), injection site swelling (>10%), and fever (>10%).

In individuals 15 months through 17 years of age vaccinated with a single dose, the most commonly reported solicited adverse reactions >10% were irritability (>60% in individuals less than 2 years of age), pain at the injection site (>50%), drowsiness (>40% in individuals less than 2 years of age), fatigue and muscle pain (>20% in individuals 2 years of age and older), decreased appetite (>20% in individuals less than 2 years of age), injection site swelling and injection site redness (>10%), headache (>10% in individuals 5 years of age and older), and fever (>10% in individuals less than 2 years of age).

In individuals 18 through 59 years of age, the most commonly reported solicited adverse reactions >10% were pain at the injection site (>70%), muscle pain (>50%), fatigue (>40%), headache (>30%), and arthralgia and injection site swelling (>10%).

In individuals 60 years of age and older, the most commonly reported solicited adverse reactions >10% were pain at the injection site (>50%), muscle pain and fatigue (>30%), headache (>20%), and arthralgia (>10%).

Clinical Trial Experience in Individuals 6 Weeks Through 17 Years of Age

The safety of Prevnar 20 in individuals from 6 weeks through 17 years of age was evaluated in 3 randomized, double-blind, active-controlled, clinical trials and one single-arm clinical trial. Across the 4 pediatric trials (Studies 8, 9, 10, and 11; NCT04382326, NCT04379713, NCT03512288, and NCT04642079, respectively) conducted in the Americas and Europe, 3063 participants received at least one dose of Prevnar 20, and 1720 participants received at least one dose of Prevnar 13.

Safety Assessment in Individuals Receiving a 4-Dose Series (Studies 8 through 10)

The safety of Prevnar 20 was assessed in 3 randomized, double-blind, active-controlled, clinical trials in participants (Studies 8, 9, and 10). Globally, 2232 participants who received at least one dose of a 4-dose series of Prevnar 20 and 1717 participants who received at least one dose of a 4-dose series of Prevnar 13 were included in the safety analysis. In the United States (US) (including the US territory of Puerto Rico [PR]), 1567 participants received at least one dose of a 4-dose series of Prevnar 20 and 1376 participants received at least one dose of a 4-dose series of Prevnar 13. Study 8 was a double-blind, active-controlled trial of safety and immunogenicity in participants randomized 1:1 to receive a 4-dose series of either Prevnar 20 (N=1001) or Prevnar 13 (N=990) at 2, 4, 6, and 12 through 15 months of age, conducted in the US and PR. Study 9 was a double-blind trial of tolerability and safety in participants randomized 2:1 to receive a 4-dose series of either Prevnar 20 (N=1000) or Prevnar 13 (N=503) at 2, 4, 6, and 12 through 15 months of age, conducted in countries in Europe, South America, and North America, including the US and PR. Study 10 was a double-blind, active-controlled multicenter trial of safety and immunogenicity in participants randomized 1:1 to receive a 4-dose series of either Prevnar 20 (N=231) or Prevnar 13 (N=227) at 2, 4, 6, and 12 months of age, conducted in the US.

Across the 3 infant trials, there were similar percentages of male (51.7% and 50.1%) and female (48.3% and 49.9%) participants among the Prevnar 20 and Prevnar 13 recipients respectively. Participant age at the first dose (median age: 64.0 days, range: 42 to 98 days; median age: 64.0 days, range 43 to 97 days) and last dose (median age: 372.0 days, range 365 to 460 days; median age: 372.0 days, range 366 to 455 days) in the Prevnar 20 and Prevnar 13 groups, respectively, was similar. The racial and ethnic distribution of the US/PR infant safety population was as follows: 73.8% of Prevnar 20 recipients were White, 12.1% Black, 1.9% Asian, and 7.5% multi-racial; 29.7% were Hispanic) with similar distribution among Prevnar 13 recipients. In the multi-country infant trial, Study 9, the participants were predominantly White (87.4%). This study also included 111 late preterm infants (>34 to <37 weeks gestational age) among the total study population 77 were in the Prevnar 20 group, and 34 in the Prevnar 13 group.

In Study 8, Pediarix [Diphtheria and Tetanus Toxoids and Acellular Pertussis Adsorbed, Hepatitis B (Recombinant) and Inactivated Poliovirus Vaccine Combined] (DTaP-HBV-IPV) and Hiberix [(Haemophilus influenzae type b Conjugate vaccine) [Hib] (Tetanus Toxoid conjugate)] were administered concomitantly with Prevnar 20 or Prevnar 13 at 2, 4, and 6 months of age; M-M-R II [Measles, Mumps, and Rubella Virus Vaccine Live] (MMR) and VARIVAX [Varicella virus vaccine live] were administered concomitantly with Prevnar 20 or Prevnar 13 at 12 through 15 months of age. In Study 10, Pediarix was administered concomitantly with Prevnar 20 or Prevnar 13 at 2, 4, and 6 months of age. In Studies 8 and 10, influenza and rotavirus vaccines were also permitted to be co-administered with Prevnar 20 or Prevnar 13 according to recommendations. The proportion of participants receiving a concomitant influenza vaccine and the proportions of participants receiving a concomitant rotavirus vaccine were similar across the two study groups in Studies 8 and 10. In Study 8, 65.8% to 87.3% of participants received a rotavirus vaccine with each of the first 3 doses of Prevnar 20; 11.7% and 10.1% of participants received an influenza vaccine with Dose 3 and Dose 4 of Prevnar 20, respectively. In Study 10, 65.3% to 94.8% of participants received a rotavirus vaccine with each of the first 3 doses of Prevnar 20; 21.4% of participants received an influenza vaccine with Dose 3 of Prevnar 20. In Study 9, US-licensed or non-US licensed routine pediatric vaccines were permitted to be given during the study, including with Prevnar 20 or Prevnar 13, according to local or national recommendations.

Across the infant trials, solicited local and systemic adverse reactions were recorded daily by parents/guardians using an electronic diary for 7 consecutive days following each vaccination. Adverse events (AEs) were reported from administration of the first dose until one month after the third dose, and from the fourth dose through one month after the fourth dose. Serious adverse events (SAEs) and newly diagnosed chronic medical conditions (NDCMCs) were reported from administration of the first dose through 6 months after the last dose.

Solicited Adverse Events in Individuals Receiving a 4-Dose Series (Study 8)

The percentage of participants in Study 8 with solicited local and systemic adverse reactions that occurred within 7 days following vaccination are shown in Tables 2 and 3. The median day of onset for local and systemic reactions was between Day 1 and Day 2 (Day 1 was the day of vaccination), and reactions resolved with a median duration between 1 to 2 (local reactions) or 3 days (systemic reactions).

Table 2. Percentage of Participants at 2, 4, 6, and 12 Through 15 Month of Age With Solicited Local Adverse Reactions Within 7 Days After Each Vaccination – Study 8 [Study 8 was conducted in the United States and the territory of Puerto Rico (NCT04382326).]
 | Dose 1 |  | Dose 2 |  | Dose 3 |  | Dose 4
 | Vaccine Group
 | Prevnar 20; (N [N = number of participants with any e-diary data reported after the specified dose. This value is the denominator for the percentage calculations.] =993); % | Prevnar 13; (N=974); % | Prevnar 20; (N=940); % | Prevnar 13; (N=924); % | Prevnar 20; (N=914); % | Prevnar 13; (N=901); % | Prevnar 20; (N=826); % | Prevnar 13; (N=815); %
Local Reaction
Pain at injection site [Mild: hurts if gently touched; moderate: hurts if gently touched with crying; severe: causes limitation of limb movement.]
Any [Any includes all participants who reported a reaction as mild, moderate, or severe during Day 1 to Day 7 after vaccination] | 49.1 | 45.3 | 44.0 | 41.7 | 38.6 | 39.0 | 35.7 | 35.8
Mild | 30.6 | 30.4 | 29.3 | 27.7 | 25.7 | 25.5 | 24.1 | 27.1
Moderate | 18.4 | 14.9 | 14.8 | 14.0 | 12.9 | 13.4 | 11.3 | 8.7
Severe | 0.1 | 0 | 0 | 0 | 0 | 0 | 0.4 | 0
Redness [Mild: >0.0 to 2.0 cm; moderate: >2.0 to 7.0 cm; severe: >7.0 cm.]
Any | 25.5 | 24.6 | 23.2 | 26.4 | 25.4 | 27.2 | 23.5 | 26.6
Mild | 21.5 | 22.3 | 21.2 | 23.1 | 21.1 | 23.5 | 19.6 | 22.0
Moderate | 4.0 | 2.4 | 2.0 | 3.4 | 4.3 | 3.7 | 3.9 | 4.7
Severe | 0 | 0 | 0 | 0 | 0 | 0 | 0 | 0
Swelling
Any | 16.4 | 18.8 | 15.5 | 17.3 | 17.1 | 17.6 | 14.9 | 17.3
Mild | 11.5 | 14.7 | 11.5 | 13.5 | 12.5 | 13.8 | 10.7 | 13.6
Moderate | 4.8 | 4.1 | 4.0 | 3.8 | 4.6 | 3.8 | 4.2 | 3.7
Severe | 0.1 | 0 | 0 | 0 | 0 | 0.1 | 0 | 0
Any local reaction [Any local reaction includes all participants who reported any injection site reaction (pain, swelling, or redness) as mild, moderate, or severe during Day 1 to Day 7 after vaccination.] | 59.8 | 56.5 | 53.1 | 52.7 | 50.8 | 49.1 | 44.8 | 45.9
Note: Local reactions were collected in the e-diary from Day 1 through Day 7 after each dose. If a severe reaction was identified by the investigator as a Grade 4 reaction at a follow-up assessment, it was also reported as an adverse reaction.

Table 3. Percentage of Participants at 2, 4, 6, and 12 Through 15 Months of Age With Solicited Systemic Adverse Reactions Within 7 Days After Each Vaccination – Study 8 [Study 8 was conducted in the United States and the territory of Puerto Rico (NCT04382326).]
 | Dose 1 |  | Dose 2 |  | Dose 3 |  | Dose 4
Vaccine Group
 | Prevnar 20; (N [N = number of participants with any e-diary data reported after the specified dose. This value is the denominator for the percentage calculations.] =993); % | Prevnar 13; (N=974); % | Prevnar 20; (N=940); % | Prevnar 13; (N=924); % | Prevnar 20; (N=914); % | Prevnar 13; (N=901); % | Prevnar 20; (N=826); % | Prevnar 13; (N=815); %
Systemic Events
Irritability [Mild: easily consolable; moderate: requiring increased attention; severe: inconsolable; crying cannot be comforted.]
Any [Any includes all participants who reported a reaction as mild, moderate, or severe during Day 1 to Day 7 after vaccination] | 70.9 | 71.7 | 71.6 | 68.8 | 64.4 | 63.0 | 61.0 | 61.1
Mild | 23.4 | 21.6 | 22.9 | 21.2 | 25.2 | 21.6 | 23.4 | 21.8
Moderate | 43.0 | 46.2 | 44.7 | 43.4 | 37.5 | 39.2 | 35.0 | 37.9
Severe | 4.5 | 3.9 | 4.0 | 4.2 | 1.8 | 2.2 | 2.7 | 1.3
Drowsiness [Mild: increased or prolonged sleeping bouts; moderate: slightly subdued interfering with daily activity; severe: disabling not interested in usual daily activity.]
Any | 67.2 | 66.0 | 54.7 | 55.6 | 44.1 | 44.1 | 39.5 | 39.5
Mild | 50.2 | 49.3 | 37.0 | 36.9 | 31.1 | 30.1 | 27.8 | 28.2
Moderate | 16.1 | 15.6 | 16.9 | 17.9 | 12.5 | 13.1 | 11.0 | 10.7
Severe | 0.9 | 1.1 | 0.7 | 0.9 | 0.5 | 0.9 | 0.6 | 0.6
Decreased Appetite [Mild: decreased interest in eating; moderate: decreased oral intake; severe: refusal to feed.]
Any | 24.4 | 23.9 | 26.4 | 23.5 | 20.6 | 22.4 | 24.8 | 25.2
Mild | 14.5 | 16.1 | 16.4 | 15.3 | 13.5 | 13.9 | 15.9 | 16.1
Moderate | 9.7 | 7.5 | 9.8 | 7.7 | 6.7 | 8.2 | 8.6 | 8.3
Severe | 0.2 | 0.3 | 0.2 | 0.5 | 0.4 | 0.3 | 0.4 | 0.7
Fever [Any systemic reaction: includes all participants who reported any fever ≥38.0°C or any other systemic reaction (irritability, drowsiness or decreased appetite) as mild, moderate, or severe during Day 1 to Day 7 after vaccination. The route of temperature measurement was to be rectal.]
≥38.0℃ | 10.3 | 7.5 | 17.3 | 16.3 | 12.6 | 13.7 | 14.5 | 14.0
≥38.0℃ to 38.4°C | 7.3 | 6.3 | 10.9 | 10.0 | 7.7 | 7.9 | 6.5 | 7.7
>38.4℃ to 38.9°C | 2.2 | 0.9 | 4.0 | 4.2 | 3.4 | 3.9 | 5.1 | 3.2
38.9℃ to 40.0°C | 0.7 | 0.3 | 2.2 | 2.2 | 1.4 | 1.9 | 2.7 | 2.9
>40.0°C | 0.1 | 0 | 0.2 | 0 | 0.1 | 0 | 0.2 | 0.1
Any systemic reaction | 85.9 | 84.5 | 82.0 | 80.5 | 74.0 | 72.6 | 70.8 | 71.2
Use of antipyretic or pain [Severity was not collected for use of antipyretic or pain medication. The numbers listed reflect yes responses (i.e., number of events reported).] | 35.1 | 33.8 | 40.7 | 41.0 | 36.3 | 36.1 | 37.5 | 36.7
Note: Systemic reactions and use of antipyretic/pain medication were collected in the e-diary from Day 1 through Day 7 after each dose. If a severe reaction was identified by the investigator as a Grade 4 reaction at a follow-up assessment, it was also reported as an adverse reaction.

Unsolicited Serious and Non-Serious Adverse Events in Individuals Receiving a 4-Dose Series (Studies 8 through 10)

Globally, across the 3 infant trials, the proportion of participants reporting 1 or more SAEs within 6 months after the fourth dose of Prevnar 20 was 4.5% (101 of 2232 participants). This was similar to the proportion of participants with SAEs after vaccination with Prevnar 13 3.7% (64 of 1717 participants). The proportions of SAEs observed from the first dose to 1 month after the third dose were 1.1% and 1.2% for Prevnar 20 and Prevnar 13, and from the fourth dose to 1 month after the fourth dose were 0.7% and 0.5% respectively. Participants in these studies may have received other US-licensed (Studies 8, 9, and 10) or non-US-licensed concomitant (Study 9) vaccines according to their local recommended schedule. In the Prevnar 20 group, two febrile seizures considered possibly related to vaccination with Prevnar 20 were reported. One case was serious and occurred 14 days after the fourth dose given with MMR and varicella vaccine. One case was non-serious and occurred 7 days after the fourth dose of Prevnar 20 in an individual with diagnosis of COVID-19 infection.

One participant experienced isolated injection site hypersensitivity (redness) within approximately 30 minutes of Prevnar 20 after each of the first 3 doses resolving on the same day, this was not observed after the fourth dose.

There were no notable patterns or imbalances between vaccine groups for specific categories of SAEs that would suggest a causal relationship to Prevnar 20.

Safety Assessment in Individuals 15 Months Through 17 Years of Age Receiving Catch-Up Vaccination (Study 11)

The safety of Prevnar 20 in individuals (15 months through 17 years of age) was assessed in a single-arm trial of safety and immunogenicity of a single dose of Prevnar 20 conducted in the United States (Study 11) (NCT 04642079). A total of 831 participants received a single dose of Prevnar 20 among the 4 age groups (≥15 to <24 months, ≥2 to <5 years, ≥5 to <10 years, and ≥10 to <18 years). Participants <5 years of age were eligible if they had received at least 3 prior doses of Prevnar 13. Routine pediatric vaccines including DTaP vaccines, Hib, hepatitis A, and influenza vaccines were permitted to be co-administered with Prevnar 20, if not feasible to separate from Prevnar 20 by 14 days. There were similar percentages of male and female participants, with the exception of a higher percentage of male than female participants (approximately 56% males) in the age groups ≥15 months to <24 months of age and ≥10 to <18 years of age. Participants were predominantly White (80.1% to 86.6%), with nearly all the other participants being Black or African American (8.3% to 12.4%) and multiracial (2.5% to 6.0%); 15.4% to 21.0% were Hispanic.

The safety assessment was consistent with that used in studies 8 through 10, with the exception of that age-applicable systemic adverse reactions were recorded. The types of solicited systemic events collected in the participants ≥15 months to <2 years of age were consistent with those collected in participants 6 weeks through 15 months of age (i.e., irritability, decreased appetite, drowsiness/increased sleep and fever), while the solicited systemic events in participants ≥2 years of age required verbal communication by the participant (i.e., fatigue, headache, muscle pain, joint pain and fever).

Solicited Adverse Reactions in Individuals 15 Months Through 17 Years of Age Receiving Catch-Up Vaccination (Study 11)

After a single dose of Prevnar 20, most local and systemic adverse reaction in individuals 15 months through 17 years of age were mild or moderate in severity and resolved within 1 to 2 days. The most frequently reported local reaction was pain at injection site (52.5%, 66.0%, 82.9%, 82.0% in individuals ≥15 months to <24 months, ≥2 to <5 years, ≥5 to <10 years, and ≥10 to <18 years respectively), followed by redness and swelling. Most local reactions were mild or moderate in severity.

The most frequently reported solicited systemic reactions in individuals ≥15 months to <2 years of age were irritability (61.8%), followed by drowsiness and increased sleep (41.7%), and decreased appetite (25.0%). Fever ≥38.0°C was reported by 11.8% of individuals; fever >38.4°C was reported infrequently.

The most frequently reported systemic events in participants ≥2 to <18 years of age varied by age group. Fatigue was most frequently reported in individuals ≥2 to <5 years of age, and muscle pain was most frequently reported in participants ≥5 to <10 years and ≥10 to <18 years of age. Fever was reported infrequently (in ≤3.3% of individuals ≥2 to <5 years of age and only 1 participant, 0.5% ≥5 to <10 years of age).

Serious Adverse Events in Individuals 15 Months Through 17 Years of Age (Study 11)

In Study 11, five participants reported SAEs within 6 months after vaccination (2 participants [1.0%] ≥15 to <24 months of age and 3 participants [1.5%] ≥10 to <18 years of age). One participant (0.5%) ≥15 to <24 months of age reported an SAE within 1 month after vaccination. No SAEs were considered related to the vaccination.

Unsolicited Adverse Reactions Following the Use of Prevnar and Prevnar 13

Events observed in clinical trials with Prevnar (Pneumococcal 7-valent Conjugate Vaccine [Diphtheria CRM197 Protein]) or Prevnar 13 in individuals 6 weeks through 15 months of age are relevant to Prevnar 20 since the vaccines are manufactured and formulated similarly and contain 7 and 13 of the same polysaccharide conjugates, respectively.

Reactions occurring in greater than 1% of infants and toddlers following administration of Prevnar 13: diarrhea, vomiting, and rash.

Reactions occurring in less than 1% of infants and toddlers following administration of Prevnar 13: crying, hypersensitivity reaction (including face edema, dyspnea, and bronchospasm), seizures (including febrile seizures), and urticaria or urticaria-like rash.

Among 6,839 participants who received at least 1 dose of Prevnar 13 in clinical trials conducted globally, there was 1 hypotonic-hyporesponsive episode adverse reaction reported (0.015%). Among 4,204 participants who received at least 1 dose of Prevnar in clinical trials conducted globally, there were 3 hypotonic-hyporesponsive episode adverse reactions reported (0.071%). All 4 events occurred in a single clinical trial in Brazil in which participants received whole cell pertussis vaccine at the same time as Prevnar 13 or Prevnar.

Clinical Trials Experience With Prevnar 20 in Individuals 18 Years of Age and Older

The safety of a single dose of Prevnar 20 in individuals 18 years of age and older was evaluated in 6 randomized, active-controlled, multicenter clinical trials and one open-label, multicenter clinical trial. All of the trials were conducted in the United States and 2 of the trials also enrolled participants (N=172) in Sweden. Across the 7 trials, 6343 individuals received Prevnar 20 and 2496 received active control vaccine.

Safety Assessments in Pneumococcal Vaccine Naïve Participants 18 Years of Age and Older (Studies 1 through 5)

The safety of Prevnar 20 in individuals 18 years of age and older with no history of pneumococcal vaccination was evaluated in 5 studies (Studies 1–5). In the main cohort of Study 1 (NCT03760146) and in Study 2 (NCT03313037), participants ≥60 years of age and participants 60 through 64 years of age, respectively, received a single dose of Prevnar 20 followed 1 month later with administration of saline placebo or received a single dose of Prevnar 13 followed 1 month later with a dose of PNEUMOVAX® 23 (PPSV23). The 2 other cohorts of Study 1, participants 50 through 59 years of age and participants 18 through 49 years of age, received a single vaccination with Prevnar 20 or Prevnar 13. In Study 3 (NCT03828617), participants 18 through 49 years of age received a single vaccination with Prevnar 20 or Prevnar 13. In Studies 4 (NCT02955160) and 5 (NCT03642847), which were smaller studies conducted early in the clinical development of Prevnar 20, participants 18 through 49 years of age received a single dose of Prevnar 20 or an active control (Tdap or Prevnar 13).

Safety Assessments in Participants ≥65 Years of Age (Pneumococcal Vaccine Naïve or Previously Immunized with a Pneumococcal Vaccine) (Studies 6 and 7)

The safety of Prevnar 20 in individuals 65 years of age and older with pneumococcal vaccination given as routine care prior to enrollment was assessed in Study 6 (NCT03835975). Participants were enrolled into 1 of 3 cohorts based on their prior pneumococcal vaccination history (PPSV23 only ≥1 to ≤5 years prior to enrollment, Prevnar 13 only ≥6 months prior to enrollment, or Prevnar 13 followed by PPSV23 [with PPSV23 given ≥1 year prior to enrollment]). Participants in 2 of the cohorts received a single vaccination with Prevnar 20 or control pneumococcal vaccine (Prevnar 13), and the other cohort received a single vaccination with Prevnar 20. only.

The safety of Prevnar 20 in individuals 65 years of age and older when coadministered with Influenza Vaccine, Adjuvanted (Fluad Quadrivalent) was assessed in Study 7 (NCT 04526574). Randomization was stratified by prior pneumococcal vaccine status (no previous pneumococcal vaccine, receipt of at least 1 dose of PPSV23 only, receipt of at least 1 dose of Prevnar 13 only, or receipt of at least 1 dose each of PPSV23 and Prevnar 13). Participants were randomized in a 1:1 ratio to receive Prevnar 20 concomitantly administered with Fluad Quadrivalent (Group 1) or Fluad Quadrivalent followed approximately one month later by Prevnar 20 (Group 2).

Demographics of Trial Participants 18 Years of Age and Older (Studies 1, 3, 6 and 7)

In the three main trials (Studies 1, 3, and 6), participants were predominantly female (52.0% to 65.9%) across groups defined by age and prior pneumococcal vaccination status within the Prevnar 20 and control vaccine groups. Across all 3 trials combined, 59.8% of participants were 60 years of age and older, 6.9% were 50 through 59 years of age, and 33.3% were 18 through 49 years of age. In Studies 1 and 3, participants were 80.7% White, 14.2% Black, 2.1% Asian, and 10.3% Hispanic. In Study 6, participants were predominantly White (92.4%). Participants were primarily from the United States; however a portion of participants 65 years of age and older were enrolled from Sweden in Study 1 (5.7% of participants 60 years of age and older in that study) and also in Study 6 (35.5% of participants with prior PPSV23 only). In Study 7, 54.7% of participants were female. The mean age of participants was 72 years (range 65–103 years). Participants were 90.6% White, 6.9% Black, 1.2% Asian, and 9.4% Hispanic.

In the three main trials, participants with pre-existing underlying diseases were enrolled if the medical condition was stable (did not require a significant change in therapy in the 6 weeks before receipt of study vaccine or any hospitalization for worsening disease within 12 weeks before receipt of study vaccine). In Study 1, approximately one-third of all participants had risk factors that placed them at increased risk for serious pneumococcal disease, including smoking (12.9%), stable medical conditions of chronic cardiovascular disease (5.5%), chronic pulmonary disease including asthma (8.7%), chronic liver disease (0.4%), and diabetes mellitus (13.9%).

Safety Monitoring

Solicited adverse reactions for Prevnar 20 in the three main trials and Study 7 were monitored in participants recording daily into an electronic diary their local adverse reactions for 10 consecutive days and systemic reactions for 7 consecutive days following vaccination. Across all trials, serious and nonserious adverse events were collected for 1 month after each vaccination. Safety follow-up of SAEs continued through 6 months after vaccination with Prevnar 20 or Prevnar 13 (or other appropriate control vaccine), as applicable. Newly diagnosed chronic medical conditions occurring within 6 months after vaccination were also collected via telephone contact.

Serious Adverse Events in Participants 18 Years of Age and Older (Studies 1 through 6)

Across studies 1 through 6, performed in individuals of all ages, naïve to and with prior pneumococcal vaccination, the proportion of participants reporting 1 or more SAEs within 6 months after vaccination with Prevnar 20 was 1.5% (67 of 4552 participants). This was similar to the proportion of participants with SAEs after vaccination with Prevnar 13 or other applicable control vaccine (1.8%, 44 of 2496). The proportions of participants with SAEs occurring within 1 month after vaccination with Prevnar 20 or with Prevnar 13 or other applicable control vaccine were both 0.4% (19 of 4552 participants and 11 of 2496 participants, respectively). There were no notable patterns or imbalances between vaccine groups for specific categories of serious adverse events that would suggest a causal relationship to Prevnar 20.

Solicited Adverse Reactions in Participants 18 Years of Age and Older (Studies 1 and 6)

The frequency and severity of the local adverse reactions (redness, swelling, and pain at the injection site) prompted daily in the 10 days after Prevnar 20 vaccination in individuals naïve to pneumococcal vaccination (Study 1) and in individuals with prior pneumococcal vaccination (Study 6) are shown in Table 4 and Table 5, respectively. The frequency and severity of the systemic adverse reactions (fever, fatigue, headache, muscle pain, and joint pain) prompted daily in the 7 days after Prevnar 20 vaccination in individuals naïve to pneumococcal vaccination (Study 1) and in individuals with prior pneumococcal vaccination (Study 6) are shown in Table 6 and Table 7, respectively.

Table 4. Percentage of Participants With Solicited Local Adverse Reactions, by Maximum Severity, Within 10 Days After Vaccination in Pneumococcal Vaccine-Naïve Individuals - Study 1 [Study 1 was conducted in the United States and in Sweden (NCT03760146).]
 | 18–49 Years of Age |  | 50–59 Years of Age |  | ≥60 Years of Age
 | Vaccine Group
 | Prevnar 20 (N [N = number of participants with any e-diary data reported after vaccination (after Vaccination 1 [Prevnar 20 or Prevnar 13] for Study 1 participants 60 years of age and older). This value is the denominator for the percentage calculations.] =335) % | Prevnar 13 (N=112) % | Prevnar 20 (N=331) % | Prevnar 13 (N=111) % | Prevnar 20/Saline (N=1505) % | Prevnar 13/PPSV23 (N=1483) %
Local Reaction
Pain at injection site [Diameters were measured in caliper units of whole numbers from 1 to 21 or 21+. One caliper unit = 0.5 cm. Measurements were rounded up to the nearest whole number. Intensity of redness and swelling were then characterized as follows: mild is >2.0 to 5.0 cm; moderate is >5.0 to 10.0 cm; severe is >10.0 cm.]
Any ["Any" includes all participants who reported a reaction as "mild", "moderate", or "severe" during Day 1 to Day 10 after vaccination.] | 81.2 | 82.1 | 72.5 | 69.4 | 55.4 | 54.1
Mild | 42.7 | 52.7 | 53.5 | 52.3 | 45.3 | 44.6
Moderate | 38.2 | 28.6 | 17.8 | 16.2 | 9.9 | 9.2
Severe | 0.3 | 0.9 | 1.2 | 0.9 | 0.2 | 0.3
Swelling [Mild = does not interfere with activity; moderate = interferes with activity; severe = prevents daily activity.]
Any (>2.0 cm) | 11.6 | 12.5 | 8.8 | 10.8 | 7.5 | 8.0
Mild | 7.2 | 8.9 | 5.7 | 7.2 | 4.8 | 4.9
Moderate | 4.5 | 3.6 | 3.0 | 3.6 | 2.4 | 2.8
Severe | 0 | 0 | 0 | 0 | 0.3 | 0.3
Redness
Any (>2.0 cm) | 9.0 | 9.8 | 8.2 | 5.4 | 7.3 | 6.2
Mild | 3.0 | 5.4 | 5.1 | 2.7 | 3.7 | 3.8
Moderate | 5.4 | 4.5 | 2.7 | 2.7 | 2.8 | 2.2
Severe | 0.6 | 0 | 0.3 | 0 | 0.8 | 0.2
Any local reaction ["Any local reaction" includes all participants who reported any injection site reaction (pain, swelling, or redness) as "mild", "moderate", or "severe" during Day 1 to Day 10 after vaccination.] | 81.2 | 82.1 | 72.8 | 70.3 | 57.4 | 56.0

Table 5. Percentage of Participants With Solicited Local Adverse Reactions, by Maximum Severity, Within 10 Days After Vaccination in Individuals 65 Years of Age and Older With Prior Pneumococcal Vaccination – Study 6 [Study 6 was conducted in the United States and in Sweden (NCT03835975)] , [Open-label administration of Prevnar 20.]
 | Prior Pneumococcal Vaccination Status [Includes participants who previously received either PPSV23 ≥1 to ≤5 years before enrollment (PPSV23), Prevnar 13 ≥6 months before enrollment (Prevnar 13), or Prevnar 13 followed by PPSV23 ≥1 year before enrollment (Prevnar 13 and PPSV23) in the study.]
 | PPSV23 |  | Prevnar 13 |  | Prevnar 13 and PPSV23
 | Vaccine Group
 | Prevnar 20 (N [N = number of participants with any e-diary data reported after vaccination. This value is the denominator for the percentage calculations.] =253) % | Prevnar 13 (N=121) % | Prevnar 20 (N=245) % | PPSV23 (N=126) % | Prevnar 20 (N=125) %
Local Reaction
Pain at the injection site [Mild = does not interfere with activity; moderate = interferes with activity; severe = prevents daily activity.]
Any ["Any" includes all participants who reported a reaction as "mild", "moderate", or "severe" during Day 1 to Day 10 after vaccination.] | 50.2 | 43.0 | 61.2 | 56.3 | 52.8
Mild | 45.8 | 38.8 | 54.7 | 40.5 | 47.2
Moderate | 4.3 | 3.3 | 6.1 | 14.3 | 5.6
Severe | 0 | 0.8 | 0.4 | 1.6 | 0
Swelling [Diameters were measured in caliper units of whole numbers from 1 to 21 or 21+. One caliper unit = 0.5 cm. Measurements were rounded up to the nearest whole number. Intensity of redness and swelling were then characterized as follows: mild is >2.0 to 5.0 cm; moderate is >5.0 to 10.0 cm; severe is >10.0 cm.]
Any (>2.0 cm) | 9.9 | 6.6 | 9.4 | 14.3 | 4.0
Mild | 5.1 | 6.6 | 5.7 | 6.3 | 1.6
Moderate | 3.6 | 0 | 3.7 | 7.1 | 2.4
Severe | 1.2 | 0 | 0 | 0.8 | 0
Redness
Any (>2.0 cm) | 7.9 | 2.5 | 8.6 | 12.7 | 4.8
Mild | 3.6 | 1.7 | 2.9 | 4.8 | 1.6
Moderate | 3.2 | 0.8 | 5.3 | 7.1 | 3.2
Severe | 1.2 | 0 | 0.4 | 0.8 | 0
Any local reaction ["Any local reaction" includes all participants who reported any injection site reaction (pain, swelling, or redness) as "mild", "moderate", or "severe" during Day 1 to Day 10 after vaccination.] | 53.0 | 43.8 | 64.1 | 57.9 | 54.4

Table 6. Percentage of Participants With Solicited Systemic Reactions, by Maximum Severity, Within 7 Days After Vaccination in Pneumococcal Vaccine-Naïve Individuals – Study 1 [Study 1 was conducted in the United States and in Sweden (NCT03760146).]
 | 18 through 49 Years of Age |  | 50 through 59 Years of Age |  | ≥60 Years of Age
 | Vaccine Group
 | Prevnar 20 (N [N = number of participants with any e-diary data reported after vaccination (after Vaccination 1 [Prevnar 20 or Prevnar 13] for Study 1 participants 60 years of age and older). This value is the denominator for the percentage calculations.] =335) % | Prevnar 13 (N=112) % | Prevnar 20 (N=331) % | Prevnar 13 (N=111) % | Prevnar 20/Saline (N=1505) % | Prevnar 13/PPSV23 (N=1483) %
Systemic Reaction
Muscle pain [Mild = does not interfere with activity; moderate = some interference with activity; severe = prevents daily activity.]
Any ["Any" includes all participants who reported a reaction as "mild", "moderate", or "severe" during Day 1 to Day 7 after vaccination.] | 66.6 | 74.1 | 49.8 | 49.5 | 39.1 | 37.3
Mild | 36.4 | 42.0 | 33.8 | 31.5 | 28.9 | 26.8
Moderate | 29.0 | 31.3 | 15.4 | 17.1 | 9.8 | 10.0
Severe | 1.2 | 0.9 | 0.6 | 0.9 | 0.4 | 0.5
Fatigue
Any | 42.7 | 43.8 | 39.3 | 36.0 | 30.2 | 30.7
Mild | 18.8 | 20.5 | 21.1 | 18.0 | 16.1 | 17.5
Moderate | 22.1 | 19.6 | 17.2 | 15.3 | 12.8 | 11.9
Severe | 1.8 | 3.6 | 0.9 | 2.7 | 1.2 | 1.2
Headache
Any | 38.8 | 33.9 | 32.3 | 36.0 | 21.5 | 23.3
Mild | 21.5 | 16.1 | 20.5 | 21.6 | 15.5 | 17.0
Moderate | 14.6 | 17.0 | 10.9 | 13.5 | 5.4 | 5.9
Severe | 2.7 | 0.9 | 0.9 | 0.9 | 0.7 | 0.3
Joint pain
Any | 13.4 | 17.9 | 15.4 | 20.7 | 12.6 | 13.7
Mild | 6.3 | 8.9 | 10.6 | 12.6 | 6.9 | 7.1
Moderate | 7.2 | 8.0 | 4.8 | 7.2 | 5.4 | 6.3
Severe | 0 | 0.9 | 0 | 0.9 | 0.3 | 0.2
Fever
≥38.0°C | 1.2 | 1.8 | 1.5 | 0.9 | 0.9 | 0.8
≥38.0°C to 38.4°C | 0.6 | 0 | 0.6 | 0.9 | 0.3 | 0.4
>38.4°C to 38.9°C | 0.3 | 0 | 0.3 | 0 | 0.3 | 0.2
>38.9°C to 40.0°C | 0.3 | 1.8 | 0.3 | 0 | 0 | 0
>40.0°C | 0 | 0 | 0.3 | 0 | 0.3 | 0.2
Any systemic reaction ["Any systemic reaction" includes all participants who reported any fever ≥38.0°C or any other systemic reaction (fatigue, headache, joint pain, or muscle pain) as "mild", "moderate", or "severe" during Day 1 to Day 7 after vaccination.] | 79.4 | 83.0 | 69.5 | 67.6 | 55.2 | 55.4
Use of antipyretic or pain medication [Severity was not collected for use of antipyretic or pain medication. The numbers listed reflect "yes" responses (i.e., number of reactions reported).] | 25.7 | 23.2 | 24.5 | 27.9 | 18.5 | 20.4

Table 7. Percentage of Participants With Solicited Systemic Reactions, by Maximum Severity, Within 7 Days After Vaccination in Individuals 65 Years of Age and Older With Prior Pneumococcal Vaccination – Study 6 [Study 6 was conducted in the United States and in Sweden (NCT03835975).] , [Open-label administration of Prevnar 20.]
 | Prior Pneumococcal Vaccination Status [Includes participants who previously received either PPSV23 ≥1 to ≤5 years before enrollment (PPSV23), Prevnar 13 ≥6 months before enrollment (Prevnar 13), or Prevnar 13 followed by PPSV23 ≥1 year before enrollment (Prevnar 13 and PPSV23) in the study.]
 | PPSV23 |  | Prevnar 13 |  | Prevnar 13 and PPSV23
 | Vaccine Group
 | Prevnar 20 (N [N = number of participants with any e-diary data reported after vaccination. This value is the denominator for the percentage calculations.] =253) % | Prevnar 13 (N=121) % | Prevnar 20 (N=245) % | PPSV23 (N=126) % | Prevnar 20 (N=125) %
Systemic Reaction
Muscle pain [Mild = does not interfere with activity; moderate = interferes with activity; severe = prevents daily activity.]
Any ["Any" includes all participants who reported a reaction as "mild", "moderate", or "severe" during Day 1 to Day 7 after vaccination.] | 32.0 | 31.4 | 33.9 | 46.0 | 37.6
Mild | 26.1 | 24.0 | 25.3 | 31.7 | 28.0
Moderate | 5.5 | 5.0 | 8.6 | 11.9 | 8.8
Severe | 0.4 | 2.5 | 0 | 2.4 | 0.8
Fatigue
Any | 28.9 | 22.3 | 31.0 | 33.3 | 32.8
Mild | 17.8 | 9.9 | 19.6 | 19.8 | 19.2
Moderate | 11.1 | 9.9 | 10.2 | 13.5 | 12.0
Severe | 0 | 2.5 | 1.2 | 0 | 1.6
Headache
Any | 17.8 | 18.2 | 13.5 | 21.4 | 19.2
Mild | 12.6 | 12.4 | 9.8 | 20.6 | 12.8
Moderate | 4.7 | 5.8 | 3.7 | 0.8 | 5.6
Severe | 0.4 | 0 | 0 | 0 | 0.8
Joint pain
Any | 6.7 | 10.7 | 11.8 | 15.9 | 16.8
Mild | 4.7 | 5.0 | 7.8 | 10.3 | 12.8
Moderate | 2.0 | 5.0 | 4.1 | 5.6 | 4.0
Severe | 0 | 0.8 | 0 | 0 | 0
Fever
≥38.0°C | 0.8 | 0 | 0 | 1.6 | 0
≥38.0°C to 38.4°C | 0.8 | 0 | 0 | 0.8 | 0
>38.4°C to 38.9°C | 0 | 0 | 0 | 0.8 | 0
>38.9°C to 40.0°C | 0 | 0 | 0 | 0 | 0
>40.0°C | 0 | 0 | 0 | 0 | 0
Any systemic reaction ["Any systemic reaction" includes all participants who reported any fever ≥38.0°C or any other systemic reaction (fatigue, headache, joint pain, or muscle pain) as "mild", "moderate", or "severe" during Day 1 to Day 7 after vaccination.] | 51.8 | 43.8 | 50.2 | 59.5 | 52.8
Use of antipyretic or pain medication [Severity was not collected for use of antipyretic or pain medication. The numbers listed reflect "yes" responses (i.e., number of reactions reported).] | 15.8 | 14.9 | 17.1 | 19.8 | 17.6

Safety with Concomitant Vaccine Administration in Participants ≥65 years of age (Study 7)

In Study 7, the rates of local reactions at the Prevnar 20 injection site within 10 days after vaccination were similar between participants who received Prevnar 20 and Fluad Quadrivalent concomitantly (Group 1) or separately (Group 2). The rates of systemic reactions within 7 days following administration of Prevnar 20 were generally numerically higher in Group 1 compared to Group 2; however, overall, fever in both groups was uncommon (<1.5%) and other systemic reactions (fatigue, headache, muscle, or joint pain) were primarily mild to moderate (≤0.9% were severe). The proportions of participants with SAEs occurring within 1 month after vaccination with Prevnar 20 were 1.1% for Group 1 and 1.7% in Group 2. No SAEs occurring within 1 month after vaccination with Prevnar 20 were considered related to vaccination.

6.2 Postmarketing Experience With Prevnar 13

The postmarketing safety experience with Prevnar 13 in individuals 6 weeks of age and older is relevant to Prevnar 20 since the vaccines are manufactured and formulated similarly and contain 13 of the same polysaccharide conjugates. These adverse reactions are included based on one or more of the following factors: severity, frequency of reporting, or strength of evidence for a causal relationship to Prevnar 13 vaccine. Because these reactions are reported voluntarily from a population of uncertain size, it is not always possible to reliably estimate their frequency or establish a causal relationship to product exposure. The following adverse reactions have been spontaneously reported during postapproval use of Prevnar 13 and may also be seen in postmarketing experience with Prevnar 20.

- Blood and lymphatic system disorders: Lymphadenopathy localized to the region of the injection site
- Cardiac disorders: Cyanosis (pediatric populations only)
- General Disorders and Administration Site Conditions: Vaccination-site dermatitis, vaccination-site pruritus, vaccination-site urticaria
- Immune System Disorders: Anaphylactic/anaphylactoid reaction, including shock
- Nervous system disorders: Hypotonia (pediatric populations only
- Respiratory: Apnea (pediatric populations only)
- Skin and Subcutaneous Tissue Disorders: Angioneurotic edema, Erythema multiforme
- Vascular disorders: Pallor (pediatric populations only)

7 DRUG INTERACTIONS

7.1 Prior Vaccination With PNEUMOVAX 23

In adults, receipt of PPSV23 1 to 5 years prior to Prevnar 20 resulted in diminished OPA geometric mean titers (GMTs) to Prevnar 20 compared to OPA GMTs in recipients who received Prevnar 13 at least 6 months prior to Prevnar 20, and compared to OPA GMTs in recipients who received Prevnar 13 followed by PPSV23, with the last dose of PPSV23 given at least 1 year prior to Prevnar 20 [see Clinical Studies (14.2)].

7.2 Immunosuppressive Therapies

Individuals with impaired immune responsiveness due to the use of immunosuppressive therapy (including irradiation, corticosteroids, antimetabolites, alkylating agents, and cytotoxic agents) may not respond optimally to Prevnar 20.

8 USE IN SPECIFIC POPULATIONS

8.1 Pregnancy

Risk Summary

All pregnancies have a risk of birth defect, loss, or other adverse outcomes. In the US general population, the estimated background risk of major birth defects and miscarriage in clinically recognized pregnancies is 2% to 4% and 15% to 20%, respectively. There are no adequate and well-controlled studies of Prevnar 20 in pregnant women. Available data on Prevnar 20 administered to pregnant women are insufficient to inform vaccine-associated risks in pregnancy.

A developmental toxicity study was performed in female rabbits administered Prevnar 20 prior to mating and during gestation. The dose was 0.5 mL at each occasion (a single human dose is 0.5 mL). This study revealed no evidence of harm to the fetus due to Prevnar 20 (see Data).

Data

Animal Data

In a developmental toxicity study, female rabbits were administered Prevnar 20 by intramuscular injection twice prior to mating (17 days and 4 days prior to mating) and twice during gestation (Gestation Days 10 and 24), 0.5 mL/rabbit/occasion (a single human dose). No adverse effects on pre-weaning development were observed. There were no vaccine-related fetal malformations or variations.

8.2 Lactation

Risk Summary

It is not known whether Prevnar 20 is excreted in human milk. Data are not available to assess the effects of Prevnar 20 on the breastfed infant or on milk production/excretion. The developmental and health benefits of breastfeeding should be considered along with the mother's clinical need for Prevnar 20 and any potential adverse effects on the breastfed child from Prevnar 20 or from the underlying maternal condition. For preventive vaccines, the underlying maternal condition is susceptibility to disease prevented by the vaccine.

8.4 Pediatric Use

The safety of Prevnar 20 has been established in individuals 6 weeks through 17 years of age [see Adverse Reactions (6.1)].

The effectiveness of Prevnar 20 for the prevention of invasive disease caused by S. pneumoniae serotypes 1, 3, 4, 5, 6A, 6B, 7F, 8, 9V, 10A, 11A, 12F, 14, 15B, 18C, 19A, 19F, 22F, 23F, and 33F has been established in individuals 6 weeks through 17 years of age [see Clinical Studies (14.2)].

The effectiveness of Prevnar 20 for the prevention of otitis media caused by serotypes 4, 6B, 9V, 14, 18C, 19F, and 23F has been established in individuals 6 weeks through 5 years of age [see Clinical Studies (14.1)].

The effectiveness of Prevnar 20 in infants and children initiating vaccination at 7 months through 17 years of age and in children 15 months through 17 years of age previously vaccinated or incompletely vaccinated with a pneumococcal conjugate vaccine is supported by evidence from clinical studies in younger children who received a 4-dose series of Prevnar 20 and by evidence from clinical studies of catch-up vaccination with Prevnar 13 and Prevnar.

The effectiveness of Prevnar 20 for the prevention of pneumonia has not been established in individuals younger than 18 years of age.

The safety and effectiveness of Prevnar 20 in individuals younger than 6 weeks of age have not been established.

8.5 Geriatric Use

Of the total number of Prevnar 20 recipients 18 years of age and older evaluated for safety in the 3 main clinical trials (N=4263), 26.7% (n=1138) were 65 years of age and older and 1.7% (n=72) were 80 years of age and older [see Clinical Studies (14.2)].

Prevnar 20 recipients 70 through 79 years of age and ≥80 years of age had lower OPA GMTs for all pneumococcal serotypes compared to Prevnar 20 recipients 18 through 49 years, 50 through 59, and 60 through 64 years of age [see Clinical Studies (14.1)].

11 DESCRIPTION

Prevnar 20, Pneumococcal 20-valent Conjugate Vaccine is a sterile suspension of saccharides of the capsular antigens of S. pneumoniae serotypes 1, 3, 4, 5, 6A, 6B, 7F, 8, 9V, 10A, 11A, 12F, 14, 15B, 18C, 19A, 19F, 22F, 23F, and 33F, individually linked to non-toxic diphtheria CRM197 protein. Each serotype is grown in soy peptone broth. The individual polysaccharides are purified by a series of chemical and physical methods. The polysaccharides are chemically activated and then directly conjugated to the carrier protein CRM197, to form the glycoconjugate. CRM197 is a non-toxic variant of diphtheria toxin isolated from cultures of Corynebacterium diphtheriae strain C7 (β197) grown in a casamino acids and yeast extract-based medium or in a chemically-defined medium. CRM197 is purified by a series of chemical and physical methods. The individual glycoconjugates are purified by a series of chemical and physical methods and analyzed for saccharide to protein ratios, molecular size, free saccharide, and free protein.

The individual glycoconjugates are compounded to formulate Prevnar 20. Potency of the formulated vaccine is determined by quantification of each of the saccharide antigens and by the saccharide to protein ratios in the individual glycoconjugates. Each 0.5 mL dose of the vaccine is formulated to contain approximately 2.2 μg of each of S. pneumoniae serotypes 1, 3, 4, 5, 6A, 7F, 8, 9V, 10A, 11A, 12F, 14, 15B, 18C, 19A, 19F, 22F, 23F, 33F saccharides, 4.4 μg of 6B saccharides, 51 μg CRM197 carrier protein, 100 μg polysorbate 80, 295 μg succinate buffer, 4.4 mg sodium chloride, and 125 μg aluminum as aluminum phosphate adjuvant.

12 CLINICAL PHARMACOLOGY

12.1 Mechanism of Action

Protection against pneumococcal disease is conferred mainly by antibodies (immunoglobulin G [IgG] directed against capsular polysaccharides) and OPA killing of S. pneumoniae. Prevnar 20 induces IgG antibodies and OPA against the 20 vaccine serotypes.

An opsonic antibody titer or serotype-specific IgG concentration that is predictive of protection against invasive pneumococcal disease or pneumococcal pneumonia has not been established.

13 NONCLINICAL TOXICOLOGY

13.1 Carcinogenesis, Mutagenesis, Impairment of Fertility

Prevnar 20 has not been evaluated for the potential to cause carcinogenicity, genotoxicity, or impairment of male fertility. Vaccination of female rabbits with Prevnar 20 had no effect on female fertility [see Use in Specific Populations (8.1)].

14 CLINICAL STUDIES

14.1 Prevnar and Prevnar 13 Efficacy Data

Efficacy and effectiveness of Prevnar and Prevnar 13 are relevant to Prevnar 20, since Prevnar, Prevnar 13 and Prevnar 20 are manufactured similarly. In addition, Prevnar and Prevnar 20 contain 7 of the same polysaccharide conjugates and Prevnar 13 and Prevnar 20 contain 13 of the same polysaccharide conjugates.

Prevnar Efficacy Data in Children

Invasive Pneumococcal Disease (IPD)

Prevnar was licensed in the United States for infants and children in 2000, following a randomized, double‑blind, clinical trial in a multiethnic population at Northern California Kaiser Permanente (NCKP) from October 1995 through August 20, 1998, in which 37,816 infants were randomized to receive either Prevnar or a control vaccine (an investigational meningococcal group C conjugate vaccine [MnCC]) at 2, 4, 6, and 12 through 15 months of age. In this study, the efficacy of Prevnar against invasive disease due to S. pneumoniae in cases accrued during this period was 100% in both the per-protocol and intent-to-treat analyses (95% confidence interval [CI]: 75.4%, 100% and 81.7%, 100%, respectively). Data accumulated through an extended follow-up period to April 20, 1999, resulted in similar efficacy estimates of 97.4% in the per-protocol analysis and 93.9% in the intent-to-treat analysis (95% CI: 82.7%, 99.9% and 79.6%, 98.5%, respectively).

Acute Otitis Media (AOM)

The efficacy of Prevnar against otitis media was assessed in 2 clinical trials: a trial in Finnish infants at the National Public Health Institute and the efficacy trial in US infants at NCKP.

The Finnish Otitis Media (FinOM) trial was a randomized, double-blind trial in which 1,662 infants were equally randomized to receive either Prevnar or a control vaccine Recombivax HB (Hepatitis B vaccine (Recombinant) [Hep B]) at 2, 4, 6, and 12 through 15 months of age. In this study, conducted between December 1995 and March 1999, parents of study participants were asked to bring their children to the study clinics if the child had respiratory infections or symptoms suggesting AOM. If AOM was diagnosed, tympanocentesis was performed, and the middle-ear fluid was cultured. If S. pneumoniae was isolated, serotyping was performed. The primary endpoint was efficacy against AOM episodes caused by vaccine serotypes in the per-protocol population.

The vaccine efficacy against AOM episodes due to vaccine serotypes assessed in the Finnish trial was 57% (95% CI: 44%, 67%) in the per-protocol population and 54% (95% CI: 41%, 64%) in the intent-to-treat population. The vaccine efficacy against AOM episodes due to vaccine-related serotypes (6A, 9N, 18B, 19A, 23A), also assessed in the Finnish trial, was 51% (95% CI: 27, 67) in the per-protocol population and 44% (95% CI: 20, 62) in the intent-to-treat population. There was a nonsignificant increase in AOM episodes caused by serotypes unrelated to the vaccine in the per-protocol population, compared to children who received the control vaccine, suggesting that children who received Prevnar appeared to be at increased risk of otitis media due to pneumococcal serotypes not represented in the vaccine. However, vaccination with Prevnar reduced pneumococcal otitis media episodes overall. In the NCKP trial, in which the endpoint was all otitis media episodes regardless of etiology, vaccine efficacy was 7% (95% CI: 4%, 10%) and 6% (95% CI: 4%, 9%), respectively, in the per-protocol and intent-to-treat analyses. Several other otitis media endpoints were also assessed in the 2 trials.

In the NCKP trial, the efficacy of Prevnar against otitis media was assessed from the beginning of the trial in October 1995 through April 1998. The otitis media analysis included 34,146 infants randomized to receive either Prevnar (N=17,070), or the control vaccine (N=17,076), at 2, 4, 6, and 12 through 15 months of age. In this trial, no routine tympanocentesis was performed, and no standard definition of otitis media was used by study physicians. The primary otitis media endpoint was efficacy against all otitis media episodes in the per‑protocol population. Recurrent AOM, defined as 3 episodes in 6 months or 4 episodes in 12 months, was reduced by 9% in both the per-protocol and intent-to-treat populations (95% CI: 3%, 15% in per-protocol and 95% CI: 4%, 14% in intent-to-treat) in the NCKP trial; a similar trend was observed in the Finnish trial. The NCKP trial also demonstrated a 20% reduction (95% CI: 2, 35) in the placement of tympanostomy tubes in the per-protocol population and a 21% reduction (95% CI: 4, 34) in the intent-to-treat population. Data from the NCKP trial accumulated through an extended follow-up period to April 20, 1999, in which a total of 37,866 children were included (18,925 in Prevnar group and 18,941 in MnCC control group), resulted in similar otitis media efficacy estimates for all endpoints.

Prevnar 13 Adult Efficacy Data

The efficacy of Prevnar 13 against vaccine-type (VT) pneumococcal community-acquired pneumonia (CAP) and IPD was assessed in a randomized, double-blind, placebo-controlled study (Community-Acquired Pneumonia Immunization Trial in Adults [CAPiTA]) conducted over ~4 years in the Netherlands. A total of 84,496 participants 65 years of age and older received a single dose of either Prevnar 13 or placebo in a 1:1 randomization; 42,240 participants were vaccinated with Prevnar 13 and 42,256 participants were vaccinated with placebo. Chronic medical conditions (asthma, diabetes, heart, liver, and/or lung diseases) were reported in 42.3% of study participants at baseline.

The primary objective was to demonstrate the efficacy of Prevnar 13 in the prevention of a first episode of confirmed VT-CAP (defined as presence of ≥2 specified clinical criteria, chest X-ray consistent with CAP as determined by a central committee of radiologists, and positive VT-specific urinary antigen detection assay [UAD] or isolation of VT S. pneumoniae from blood or other sterile site). The secondary objectives were to demonstrate the efficacy of Prevnar 13 in the prevention of a first episode of 1) confirmed nonbacteremic/noninvasive (NB/NI) VT-CAP (an episode of VT-CAP for which the blood culture result and any other sterile site culture results were negative for S. pneumoniae) and 2) VT-IPD (the presence of S. pneumoniae in a sterile site).

Surveillance for suspected pneumonia and IPD began immediately after vaccination and continued through identification of a prespecified number of cases. Participants who had a CAP or IPD episode with symptom onset less than 14 days after vaccination were excluded from all analyses.

The median duration of follow-up per participant was 3.93 years. Prevnar 13 demonstrated statistically significant vaccine efficacy (VE) in preventing first episodes of VT pneumococcal CAP, NB/NI VT pneumococcal CAP, and VT-IPD (see Table 8).

Table 8. Vaccine Efficacy for the Primary and Secondary Efficacy Endpoints – Per-Protocol Population
 |  | Vaccine Group
 |  | Prevnar 13 | Placebo
 |  | N=42,240 | N=42,256
Efficacy Endpoint | Total Number of Episodes | n | N | VE (%) | (95.2% CI)
Primary endpoint: First case of confirmed VT pneumococcal CAP | 139 | 49 | 90 | 45.6 | (21.8, 62.5)
Secondary endpoint: First episode of confirmed NB/NI VT pneumococcal CAP | 93 | 33 | 60 | 45 | (14.2, 65.3)
Secondary endpoint: First episode of VT-IPD | 35 | 7 | 28 | 75 | (41.1, 90.9)
Abbreviations: CAP = community-acquired pneumonia; CI = confidence interval; NB/NI = nonbacteremic/noninvasive; IPD = invasive pneumococcal disease; VE = vaccine efficacy; VT = vaccine-type.

14.2 Prevnar 20 Clinical Trials in Individuals 6 Weeks Through 15 Months of Age

Immunogenicity of Prevnar 20 in Individuals 6 Weeks Through 15 Months of Age

Prevnar 20 effectiveness against invasive pneumococcal disease in individuals 6 weeks through 15 months of age was demonstrated based on comparisons of serotype-specific antibody responses at 1 month after Dose 3 and 1 month after Dose 4 of Prevnar 20 to the antibody responses after vaccination with Prevnar 13.

Antibody responses elicited by Prevnar 20 and Prevnar 13 in these age groups were measured using a serotype-specific multiplex direct-binding Luminex® immunoassay (dLIA), designed to determine the concentration of serotype-specific polysaccharide-binding IgG antibodies, and OPA assays to measure serotype-specific functional OPA titers for the 20 pneumococcal serotypes of Prevnar 20. A serotype-specific IgG antibody concentration corresponding to ≥0.35 µg/mL using the World Health Organization (WHO) enzyme linked immunosorbent assay (ELISA) has been used as the threshold value for the clinical evaluation of pneumococcal conjugate vaccines when measured one month after Dose 3 of the 4-dose immunization series. The dLIA, used to measure the IgG antibody concentration, was bridged to the WHO ELISA to establish dLIA specific threshold values for each vaccine serotype that correspond to the established ≥0.35 µg/mL WHO ELISA threshold value.

In Study 8, a multicenter, randomized, active-controlled, double-blind trial, participants were randomized in a 1:1 ratio to receive Prevnar 20 (N=1004) or Prevnar 13 (N=993) in a 4-dose schedule; vaccine was administered at 2, 4, 6, and 12 through 15 months of age. Pediarix and Hiberix were administered concomitantly with each of the 3 infant doses. M-M-R II and VARIVAX were administered with the fourth dose [see Adverse Reactions (6.1) and Clinical Studies (14.3)].

Study 8 assessed serotype-specific IgG response rates, IgG geometric mean concentrations (GMCs) and OPA GMTs measured at one month after Dose 3 and one month after Dose 4 for all 20 serotypes contained in Prevnar 20. For each of the 13 matched serotypes, IgG response in the Prevnar 20 group were compared with the corresponding response in the Prevnar 13 group. For the 7 additional serotypes (serotypes 8, 10A, 11A, 12F, 15B, 22F, and 33F), IgG response in the Prevnar 20 group were compared with the lowest response among the 13 matched vaccine serotypes excluding serotype 3 in the Prevnar 13 group.

Pneumococcal IgG Antibody Responses Following 3 Doses of Prevnar 20

IgG antibody responses following Prevnar 20 were noninferior to those following Prevnar 13 for 8 of the 13 matched serotypes and 6 of the 7 additional serotypes, as assessed by the percentage of participants meeting the predefined serotype-specific IgG concentration one month after Dose 3, using a 10% noninferiority criterion (the lower bound of the 2-sided 95% CI for the difference in percentages [Prevnar 20 minus Prevnar 13] greater than -10%). Five of the 13 matched serotypes (serotypes 1, 3, 4, 9V and 23F) did not meet the pre-specified noninferiority criterion, as the lower bounds of the 2-sided 95% CIs for the difference in percentages (Prevnar 20 minus Prevnar 13) were -12.1%, -20.1%, -12.0%, -11.3%, and -11.4% respectively. One additional serotype (serotype 12F) also did not meet the NI criterion when compared to serotype 23F (the Prevnar 13 serotype with the lowest percentage excluding serotype 3) in the Prevnar 13 group, the lower bound of the 2-sided 95% CI for the difference in percentage (Prevnar 20 minus lowest Prevnar 13) was -41.6% (Table 9).

Additional IgG GMC data at one month after Dose 3 and OPA data at one month after Dose 3, presented in Tables 10 and 12 respectively, support the effectiveness of Prevnar 20 for each of the 6 serotypes that failed to meet the pre-specified non-inferiority criterion.

Table 9. Percentage of Participants Meeting Predefined Serotype-Specific Pneumococcal IgG Concentrations One Month After Dose 3 in Participants Vaccinated at 2, 4, and 6 Months of Age – Study 8 [Study 8 was conducted in the United States and the territory of Puerto Rico (NCT04382326).]
 | Prevnar 20; N [N = number of participants with valid assay results. These values are the denominators for the corresponding percentage calculations.] =831-833 | Prevnar 13; N=801-802 | Prevnar 20 minus Prevnar 13
 | % (95% CI [Exact 2-sided CI, based on the Clopper and Pearson method.]) | % (95% CI) | Percentage Difference [Noninferiority for a serotype was met if the lower bound of the 2-sided CI for the percentage difference (Prevnar 20 minus Prevnar 13) >-10% (10% NI criterion) for that serotype.] (95% CI, [2-Sided CI based on the Miettinen and Nurminen method for the difference in proportions, expressed as a percentage.])
Serotypes
1 | 79.8 (76.9, 82.5) | 88.4 (86.0, 90.5) | -8.6 (-12.1, -5.1)
3 | 52.1 (48.6, 55.5) | 67.6 (64.2, 70.8) | -15.5 (-20.1, -10.8)
4 | 79.7 (76.8, 82.4) | 88.2 (85.7, 90.3) | -8.4 (-12.0, -4.9)
5 | 82.5 (79.7, 85.0) | 86.8 (84.2, 89.1) | -4.3 (-7.8, -0.8)
6A | 93.5 (91.6, 95.1) | 95.9 (94.3, 97.2) | -2.4 (-4.6, -0.2)
6B | 88.3 (85.9, 90.4) | 92.4 (90.3, 94.1) | -4.1 (-7.0, -1.2)
7F | 96.6 (95.2, 97.8) | 97.6 (96.3, 98.6) | -1.0 (-2.7, 0.7)
9V | 81.9 (79.1, 84.4) | 89.8 (87.5, 91.8) | -7.9 (-11.3, -4.6)
14 | 93.4 (91.5, 95.0) | 94.1 (92.3, 95.7) | -0.8 (-3.1, 1.6)
18C | 92.6 (90.6, 94.2) | 93.1 (91.2, 94.8) | -0.6 (-3.1, 1.9)
19A | 97.1 (95.7, 98.1) | 98.1 (96.9, 98.9) | -1.0 (-2.6, 0.5)
19F | 96.9 (95.5, 98.0) | 96.6 (95.1, 97.8) | 0.2 (-1.5, 2.0)
23F | 77.9 (74.9, 80.7) | 85.5 (82.9, 87.9) | -7.6 (-11.4, -3.9)
Additional Serotypes [For the 7 additional serotypes, the percentage of participants with the predefined IgG concentration to serotype 23F (Prevnar 13 serotype with the lowest percentage, excluding serotype 3) in the Prevnar 13 group was used in the calculation of the percentage difference.]
8 | 96.8 (95.3, 97.9) | [For the 7 additional serotypes, percentages of participants with predefined IgG concentrations to serotypes 8, 10A, 11A, 12F, 15B, 22F and 33F in the Prevnar 13 group were 1.6%, 1.2%, 1.5%, 0.1%, 2.6%, 0.9% and 1.1%, respectively.] | 11.2 (8.6, 14.0)
10A | 82.2 (79.5, 84.8) |  | -3.3 (-6.9, 0.3)
11A | 92.7 (90.7, 94.4) |  | 7.1 (4.2, 10.2)
12F | 48.0 (44.6, 51.5) |  | -37.5 (-41.6, -33.3)
15B | 98.2 (97.0, 99.0) |  | 12.7 (10.2, 15.4)
22F | 98.3 (97.2, 99.1) |  | 12.8 (10.3, 15.5)
33F | 86.7 (84.2, 88.9) |  | 1.1 (-2.2, 4.5)
Abbreviation: IgG = immunoglobulin G.
Note: The predefined IgG concentration was ≥0.35 µg/mL for all serotypes except for serotypes 5, 6B, 12F, and 19A which were ≥0.23 µg/mL, ≥0.10 µg/mL, ≥0.69 µg/mL and ≥0.12 µg/mL respectively.

At 1 month after Dose 3, IgG GMCs in the Prevnar 20 group were noninferior to the corresponding IgG GMCs in the Prevnar 13 group for all 20 vaccine serotypes, including the 6 serotypes that missed the noninferiority criterion based on the percentage of participants meeting pre-defined IgG concentrations at one month after Dose 3. For each of the 13 matched serotypes, IgG GMCs in the Prevnar 20 group were noninferior to the corresponding IgG GMCs in the Prevnar 13 group. For each of the 7 additional serotypes, IgG GMCs in the Prevnar 20 group were noninferior to the IgG GMC for serotype 19A (the lowest result among the 13 matched vaccine serotypes excluding serotype 3) in the Prevnar 13 group (Table 10).

Table 10. Serotype-Specific Pneumococcal IgG GMCs (µg/mL) and GMC Ratios One Month After Dose 3 in Participants Vaccinated at 2, 4, 6 and 12 through 15 Months of Age – Study 8 [Study 8 was conducted in the United States and the territory of Puerto Rico (NCT04382326).]
Pneumococcal Serotype | Prevnar 20; N [N = Number of participants with valid IgG concentrations.] =831-833 | Prevnar 13; N=801-802 | Prevnar 20/Prevnar 13
 | GMC [GMCs and 2-sided CIs were calculated by exponentiating the mean logarithm of the concentrations and the corresponding CIs (based on the Student t distribution).] (95% CI) | GMC (95% CI) | GMC Ratio [Noninferiority for a serotype was met if the lower bound of the 2-sided CI of IgG GMC ratio (Prevnar 20/Prevnar 13) >0.5 (2-fold NI criterion) for that serotype.] (95% CI [2-Sided CIs were calculated by exponentiating the mean differences of the logarithms of the IgG concentrations (Prevnar 20 minus Prevnar 13) and the corresponding CIs (based on the Student t distribution).])
Serotype
1 | 0.74 (0.70, 0.79) | 1.14 (1.06, 1.22) | 0.65 (0.59, 0.72)
3 | 0.36 (0.33, 0.38) | 0.51 (0.48, 0.55) | 0.70 (0.64, 0.76)
4 | 0.75 (0.70, 0.81) | 1.08 (1.00, 1.17) | 0.70 (0.63, 0.78)
5 | 0.66 (0.61, 0.71) | 0.96 (0.88, 1.04) | 0.69 (0.61, 0.77)
6A | 1.95 (1.81, 2.10) | 2.69 (2.48, 2.92) | 0.72 (0.65, 0.81)
6B | 0.61 (0.55, 0.68) | 1.02 (0.91, 1.14) | 0.60 (0.51, 0.70)
7F | 1.71 (1.62, 1.81) | 2.29 (2.16, 2.43) | 0.75 (0.69, 0.81)
9V | 0.87 (0.81, 0.93) | 1.21 (1.12, 1.30) | 0.72 (0.65, 0.80)
14 | 2.16 (2.01, 2.33) | 2.72 (2.51, 2.95) | 0.79 (0.71, 0.89)
18C | 1.31 (1.23, 1.39) | 1.71 (1.59, 1.84) | 0.77 (0.70, 0.84)
19A | 0.72 (0.67, 0.76) | 0.91 (0.85, 0.97) | 0.79 (0.72, 0.86)
19F | 1.59 (1.50, 1.67) | 2.00 (1.88, 2.12) | 0.79 (0.73, 0.86)
23F | 0.82 (0.75, 0.90) | 1.25 (1.14, 1.37) | 0.66 (0.58, 0.75)
Additional Serotypes [For the 7 additional serotypes, the IgG GMC to serotype 19A (Prevnar 13 serotype with the lowest IgG GMC, excluding serotype 3) in the Prevnar 13 group was used in the calculation of the GMC ratio.]
8 | 1.80 (1.70, 1.91) | [For the 7 additional serotypes, the IgG GMCs to serotypes 8, 10A, 11A, 12F, 15B, 22F and 33F in the Prevnar 13 group were 0.02 µg/mL, 0.01 µg/mL, 0.02 µg/mL, 0.01 µg/mL, 0.03 µg/mL, 0.01 µg/mL and 0.02 µg/mL, respectively.] | 1.98 (1.81, 2.16)
10A | 1.21 (1.09, 1.33) |  | 1.32 (1.18, 1.49)
11A | 1.39 (1.30, 1.48) |  | 1.52 (1.39, 1.67)
12F | 0.55 (0.50, 0.60) |  | 0.60 (0.54, 0.67)
15B | 4.40 (4.11, 4.71) |  | 4.82 (4.39, 5.30)
22F | 3.71 (3.45, 3.99) |  | 4.06 (3.68, 4.48)
33F | 1.49 (1.36, 1.64) |  | 1.64 (1.46, 1.83)
Abbreviations: GMC = geometric mean concentration; IgG = immunoglobulin G; LLOQ = lower limit of quantitation.
Note: Assay results below the LLOQ were set to 0.5 × LLOQ in the analysis.

Pneumococcal IgG Antibody Responses Following 4 Doses of Prevnar 20

For each of the 13 matched serotypes, IgG GMCs in the Prevnar 20 group were noninferior to the corresponding IgG GMCs in the Prevnar 13 group. For each of the 7 additional serotypes, IgG GMCs in the Prevnar 20 group were noninferior to the IgG GMC for serotype 1 (the lowest result among the 13 matched vaccine serotypes excluding serotype 3) in the Prevnar 13 group (Table 11).

Table 11. Serotype-Specific Pneumococcal IgG GMCs (µg/mL) and GMC Ratios One Month After Dose 4 in Participants Vaccinated at 2, 4, 6 and 12 through 15 Months of Age – Study 8 [Study 8 was conducted in the United States and the territory of Puerto Rico (NCT04382326).]
 | Prevnar 20 N [N = Number of participants with valid IgG concentrations.] =753-755 | Prevnar 13 N=744-745 | Prevnar 20/Prevnar 13
 | GMC [GMCs and 2-sided CIs were calculated by exponentiating the mean logarithm of the concentrations and the corresponding CIs (based on the Student t distribution).] (95% CI) | GMC (95% CI) | GMC Ratio [Noninferiority for a serotype was met if the lower bound of the 2-sided CI of IgG GMC ratio (Prevnar 20/Prevnar 13) >0.5 (2-fold NI criterion) for that serotype.] (95% CI [2-Sided CIs were calculated by exponentiating the mean differences of the logarithms of the IgG concentrations (Prevnar 20 minus Prevnar 13) and the corresponding CIs (based on the Student t distribution).])
Serotypes
1 | 1.47 (1.37, 1.57) | 2.12 (1.97, 2.27) | 0.69 (0.63, 0.76)
3 | 0.56 (0.53, 0.60) | 0.85 (0.80, 0.90) | 0.66 (0.61, 0.73)
4 | 3.77 (3.52, 4.04) | 4.84 (4.50, 5.22) | 0.78 (0.70, 0.86)
5 | 1.87 (1.74, 2.00) | 2.51 (2.33, 2.70) | 0.74 (0.67, 0.82)
6A | 9.01 (8.45, 9.61) | 11.69 (10.91, 12.53) | 0.77 (0.70, 0.85)
6B | 4.01 (3.70, 4.35) | 5.74 (5.27, 6.24) | 0.70 (0.62, 0.79)
7F | 3.91 (3.70, 4.14) | 5.18 (4.88, 5.49) | 0.76 (0.70, 0.82)
9V | 3.44 (3.23, 3.67) | 4.30 (4.02, 4.59) | 0.80 (0.73, 0.88)
14 | 5.68 (5.27, 6.12) | 6.34 (5.88, 6.83) | 0.90 (0.81, 1.00)
18C | 3.46 (3.24, 3.70) | 4.69 (4.34, 5.05) | 0.74 (0.67, 0.82)
19A | 3.53 (3.30, 3.77) | 4.13 (3.84, 4.45) | 0.85 (0.77, 0.94)
19F | 5.01 (4.68, 5.36) | 5.79 (5.36, 6.25) | 0.86 (0.78, 0.96)
23F | 3.95 (3.63, 4.31) | 6.18 (5.66, 6.75) | 0.64 (0.57, 0.72)
Additional Serotypes [For the 7 additional serotypes, the IgG GMC to serotype 1 (Prevnar 13 serotype with the lowest IgG GMC, excluding serotype 3) in the Prevnar 13 group was used in the calculation of the GMC ratio.]
8 | 3.97 (3.73, 4.22) | [For the 7 additional serotypes, the IgG GMCs to serotypes 8, 10A, 11A, 12F, 15B, 22F and 33F in the Prevnar 13 group were 0.03 µg/mL, 0.01 µg/mL, 0.02 µg/mL, 0.01 µg/mL, 0.02 µg/mL, 0.00 µg/mL and 0.01 µg/mL, respectively.] | 1.87 (1.71, 2.06)
10A | 6.22 (5.75, 6.72) |  | 2.94 (2.64, 3.26)
11A | 3.53 (3.31, 3.78) |  | 1.67 (1.51, 1.84)
12F | 1.85 (1.73, 1.99) |  | 0.88 (0.79, 0.97)
15B | 12.59 (11.78, 13.45) |  | 5.95 (5.39, 6.55)
22F | 10.60 (9.92, 11.33) |  | 5.01 (4.54, 5.52)
33F | 9.31 (8.71, 9.96) |  | 4.40 (3.99, 4.85)
Abbreviations: GMC = geometric mean concentration; IgG = immunoglobulin G; LLOQ = lower limit of quantitation.
Note: Assay results below the LLOQ were set to 0.5 × LLOQ in the analysis.

Opsonophagocytic Activity Responses After 3 and 4 doses of Prevnar 20

Serotype-specific OPA GMTs at 1 month after Dose 3 and 1 month after Dose 4 were descriptively evaluated in a subset of participants who had received Prevnar 20 and Prevnar 13 in Study 8 (Table 12). For serotypes 1, 3, 4, 9V, 23F and 12F, for which non-inferiority was not met 1 month after Dose 3 (for the percentage of participants meeting the pre-defined serotype-specific IgG concentration), OPA GMTs at 1 month after Dose 3 were numerically similar across groups for the 5 matched serotypes and an OPA antibody response was generated to additional serotype 12F.

Table 12. Pneumococcal OPA GMTs One Month After Dose 3 and Dose 4 of a 4-Dose Series– Study 8 [Study 8 was conducted in the United States and the territory of Puerto Rico (NCT04382326).]
 | Prevnar 20; N [N = Number of participants with valid OPA titers.] = 85-105; After Dose 3 | Prevnar 13; N = 84-113; After Dose 3 | Prevnar 20; N = 80-99; After Dose 4 | Prevnar 13; N = 77-103; After Dose 4
 | GMT [GMTs and 2-sided CIs were calculated by exponentiating the mean logarithm of the titers and the corresponding CIs (based on the Student t distribution).] (95% CI) | GMT (95% CI) | GMT (95% CI) | GMT (95% CI)
Serotypes
1 | 26 (21, 33) | 34 (27, 42) | 36 (27, 48) | 66 (50, 87)
3 | 51 (43, 61) | 63 (53, 76) | 62 (49, 78) | 102 (86, 120)
4 | 339 (252, 455) | 280 (207, 378) | 621 (435, 887) | 961 (714, 1294)
5 | 32 (27, 39) | 39 (32, 47) | 55 (45, 67) | 69 (54, 87)
6A | 910 (763, 1084) | 936 (757, 1156) | 1384 (1092, 1753) | 1767(1329, 2348)
6B | 318 (242, 419) | 516 (409, 651) | 666 (489, 906) | 1211 (861, 1703)
7F | 1222 (1020, 1465) | 1149 (926, 1424) | 2022 (1673, 2444) | 2099 (1741, 2531)
9V | 661 (482, 906) | 594 (421, 838) | 2609 (1913, 3558) | 3210 (2500, 4123)
14 | 415 (323, 535) | 420 (330, 535) | 667 (523, 850) | 593 (462, 761)
18C | 1153 (910, 1460) | 996 (754, 1317) | 1973 (1472, 2643) | 2425 (1914, 3072)
19A | 108 (78, 149) | 109 (79, 151) | 844 (622, 1145) | 1357 (1007, 1829)
19F | 84 (67, 105) | 116 (90, 149) | 246 (179, 337) | 373 (272, 513)
23F | 255 (186, 350) | 295 (215, 406) | 827 (554, 1235) | 1532 (1118, 2100)
Additional Serotypes
8 | 665 (503, 880) | 18 (17, 20) | 1228 (901, 1673) | 26 (21, 31)
10A | 2558 (1869, 3501) | 37 (33, 42) | 3674 (2746, 4916) | 57 (44, 74)
11A | 289 (212, 395) | 50 (46, 55) | 2728 (1975, 3768) | 69 (53, 89)
12F | 7677 (5952, 9901) | 28 (24, 33) | 9320 (7037, 12343) | 31 (26, 37)
15B | 1560 (1090, 2233) | 18 (16, 22) | 3035 (2138, 4308) | 23 (17, 30)
22F | 6797 (5170, 8936) | 9 (9, 9) | 11077 (7956, 15422) | 15 (11, 20)
33F | 7388 (4803, 11365) | 198 (177, 220) | 19216 (13193, 27990) | 363 (292, 451)
Abbreviations: GMT = geometric mean titer; LLOQ = lower limit of quantitation; OPA = opsonophagocytic activity.
Note: Assay results below the LLOQ were set to 0.5 × LLOQ in the analysis.
Note: OPA titers were determined on serum from randomly selected subsets of participants assuring equal representation of both vaccine groups.

14.3 Prevnar 20 Clinical Trials in Individuals 18 Years of Age and Older

Immunogenicity of Prevnar 20 in Pneumococcal Vaccine Naïve Individuals

Prevnar 20 effectiveness in adults against invasive pneumococcal disease caused by the 20 vaccine serotypes and against pneumonia caused by the 13 serotypes in Prevnar 13 was demonstrated based on comparative immunogenicity to US-licensed pneumococcal vaccines (Prevnar 13 and PPSV23). Study 1, conducted in the United States and Sweden, was designed to evaluate immunologic noninferiority of Prevnar 20 to Prevnar 13 (for the 13 original S. pneumoniae serotypes) and PPSV23 (for the 7 new S. pneumoniae serotypes) in pneumococcal vaccine naive individuals ≥60 years of age. Antibody responses elicited by Prevnar 20 and the control pneumococcal vaccines were measured by serotype-specific serum OPA assays for the 20 pneumococcal serotypes at 1-month post-vaccination. OPA assays were used to measure functional antibodies to S. pneumoniae.

Study 1 included healthy individuals and immunocompetent individuals with stable underlying conditions, including chronic cardiovascular disease, chronic pulmonary disease, renal disorders, diabetes mellitus, chronic liver disease, and medical risk conditions and behaviors (e.g., smoking) that are known to increase the risk of serious pneumococcal pneumonia and IPD. A stable medical condition was defined as a medical condition not requiring significant change in therapy in the previous 6 weeks (i.e., change to new therapy category due to worsening disease) or any hospitalization for worsening disease within 12 weeks before receipt of the study vaccine.

Comparison of Immune Responses of Prevnar 20 to Prevnar 13 and PPSV23 in Pneumococcal Vaccine Naïve Individuals ≥60 Years of Age

In a randomized, active-controlled, double-blind noninferiority clinical trial (Study 1) of Prevnar 20 in the United States and Sweden, pneumococcal vaccine -naïve individuals 18 years of age and older were enrolled into 1 of 3 cohorts based on their age at enrollment and randomized to receive either Prevnar 20 or control. Participants 60 years of age and older were randomly assigned (1:1 ratio) to Prevnar 20 followed 1 month later with saline placebo or to Prevnar 13 followed 1 month later with PPSV23.

Serotype-specific OPA GMTs were measured before the first vaccination and 1 month after each vaccination. Noninferiority of immune responses, OPA GMTs 1 month after vaccination, with Prevnar 20 to a control vaccine for a serotype was declared if the lower bound of the 2 sided 95% CI for the GMT ratio (Prevnar 20/Prevnar 13; Prevnar 20/PPSV23) for that serotype was greater than 0.5.

In individuals 60 years of age and older, immune responses to all 13 matched serotypes elicited by Prevnar 20 were noninferior to the immune responses to the serotypes elicited by Prevnar 13 one month after vaccination. Immune responses to 6 out of the 7 additional serotypes induced by Prevnar 20 were noninferior to the immune responses to these same serotypes induced by PPSV23 one month after vaccination. The response to serotype 8 missed the prespecified statistical noninferiority criterion by a small margin (the lower bound of the 2-sided 95% CI for the GMT ratio being 0.49 versus >0.50) (Table 13).

In supportive analyses, 77.8% of participants in the Prevnar 20 group achieved a ≥4-fold rise in serotype 8 OPA titers from before vaccination to 1 month post-vaccination.

Table 13. OPA GMTs 1 Month After Vaccination in Participants 60 Years of Age and Older Given Prevnar 20 Compared to Prevnar 13 for the 13 Matched Serotypes and PPSV23 for the 7 Additional Serotypes (Study 1) [Study 1 was conducted in the United States and in Sweden (NCT03760146).] , [Noninferiority for a serotype was met if the lower bound of the 2-sided 95% CI for the GMT ratio (ratio of Prevnar 20/comparator) was greater than 0.5 (2-fold criterion for noninferiority).] , [Assay results below the LLOQ were set to 0.5 × LLOQ in the analysis.] , [Evaluable immunogenicity population.]
 | Prevnar 20 (N = 1157–1430) | Prevnar 13 (N = 1390–1419) | PPSV23 (N = 1201–1319) | Vaccine Comparison
 | GMT [GMTs, GMT ratios, and the associated 2-sided CIs were based on analysis of log-transformed OPA titers using a regression model with vaccine group, sex, smoking status, age at vaccination in years, and baseline log-transformed OPA titers.] | GMT | GMT | GMT Ratio (95% CI)
Serotype
1 | 123 | 154 |  | 0.80 (0.71, 0.90)
3 | 41 | 48 |  | 0.85 (0.78, 0.93)
4 | 509 | 627 |  | 0.81 (0.71, 0.93)
5 | 92 | 110 |  | 0.83 (0.74, 0.94)
6A | 889 | 1165 |  | 0.76 (0.66, 0.88)
6B | 1115 | 1341 |  | 0.83 (0.73, 0.95)
7F | 969 | 1129 |  | 0.86 (0.77, 0.96)
9V | 1456 | 1568 |  | 0.93 (0.82, 1.05)
14 | 747 | 747 |  | 1.00 (0.89, 1.13)
18C | 1253 | 1482 |  | 0.85 (0.74, 0.97)
19A | 518 | 645 |  | 0.80 (0.71, 0.90)
19F | 266 | 333 |  | 0.80 (0.70, 0.91)
23F | 277 | 335 |  | 0.83 (0.70, 0.97)
Additional Serotypes
8 | 466 |  | 848 | 0.55 (0.49, 0.62)
10A | 2008 |  | 1080 | 1.86 (1.63, 2.12)
11A | 4427 |  | 2535 | 1.75 (1.52, 2.01)
12F | 2539 |  | 1717 | 1.48 (1.27, 1.72)
15B | 2398 |  | 769 | 3.12 (2.62, 3.71)
22F | 3666 |  | 1846 | 1.99 (1.70, 2.32)
33F | 5126 |  | 3721 | 1.38 (1.21, 1.57)
Abbreviations: CI = confidence interval; GMT = geometric mean titer; LLOQ = lower limit of quantitation; N = number of participants; OPA = opsonophagocytic activity; PPSV23 = pneumococcal polysaccharide vaccine (23-valent).

Immunobridging in Pneumococcal Vaccine Naïve Individuals 18 Through 59 Years of Age

In Study 1 (described above), the effectiveness of Prevnar 20 in individuals 50 through 59 years of age and in individuals 18 through 49 years of age was inferred following comparison of the immune response to each of the 20 vaccine serotypes in each of these age groups to the corresponding serotype-specific immune responses in individuals 60 through 64 years of age following Prevnar 20 (immunobridging). In Study 1, pneumococcal vaccine-naïve participants 50 through 59 years of age and 18 through 49 years of age were randomly assigned (3:1 ratio) to receive 1 vaccination with Prevnar 20 or Prevnar 13. Serotype-specific OPA GMTs were measured before vaccination and 1 month after vaccination. A comparative analysis of Prevnar 20 in the younger age group versus Prevnar 20 in individuals 60 through 64 years of age for each vaccine serotype was performed to support the indication in individuals 18 through 49 years of age and 50 through 59 years of age. Immunobridging was to be declared successful if the lower bound of the 2-sided 95% CI for the GMT ratio (Prevnar 20 in participants 18 through 49 years of age/60 through 64 years of age and in participants 50 through 59 years of age/60 through 64 years of age) for the 20 serotypes was >0.5 (2-fold). Prevnar 20 elicited serotype-specific immune responses to each of the 20 vaccine serotypes in both of the younger age groups that were within 2-fold of the corresponding serotype-specific responses in individuals 60 through 64 years of age, when measured 1 month after vaccination (Table 14).

Table 14. Comparisons of OPA GMTs 1 Month After Prevnar 20 in Participants 18 Through 49 or 50 Through 59 Years of Age to Participants 60 Through 64 Years of Age (Study 1) [Study 1 was conducted in the United States and in Sweden (NCT03760146).] , [Immunobridging for a serotype was met if the lower bound of the 2-sided 95% CI for the GMT ratio (ratio of younger age group/60 through 64 years of age group) was greater than 0.5 (2-fold success criterion).] , [Assay results below the LLOQ were set to 0.5 × LLOQ in the analysis.] , [Evaluable immunogenicity population.]
 | 18–49 Years (N = 251–317) | 60–64 Years (N = 765–941) | 18–49 Years Relative to 60–64 Years | 50–59 Years (N = 266–320) | 60–64 Years (N = 765–941) | 50–59 Years Relative to 60–64 Years
 | GMT [GMTs, GMT ratios, and the associated 2-sided CIs were based on analysis of log-transformed OPA titers using a regression model with age group, sex, smoking status, and baseline log-transformed OPA titers. The comparisons between individuals 18 through 49 years of age and individuals 60 through 64 years of age and between individuals 50 through 59 years of age and individuals 60 through 64 years of age were based on separate regression models.] | GMT | GMT Ratio (95% CI) | GMT | GMT | GMT Ratio (95% CI)
Serotype
1 | 163 | 132 | 1.23 (1.01, 1.50) | 136 | 132 | 1.03 (0.84, 1.26)
3 | 42 | 42 | 1.00 (0.87, 1.16) | 43 | 41 | 1.06 (0.92, 1.22)
4 | 1967 | 594 | 3.31 (2.65, 4.13) | 633 | 578 | 1.10 (0.87, 1.38)
5 | 108 | 97 | 1.11 (0.91, 1.36) | 85 | 97 | 0.88 (0.72, 1.07)
6A | 3931 | 1023 | 3.84 (3.06, 4.83) | 1204 | 997 | 1.21 (0.95, 1.53)
6B | 4260 | 1250 | 3.41 (2.73, 4.26) | 1503 | 1199 | 1.25 (1.00, 1.56)
7F | 1873 | 1187 | 1.58 (1.30, 1.91) | 1047 | 1173 | 0.89 (0.74, 1.07)
9V | 6041 | 1727 | 3.50 (2.83, 4.33) | 1726 | 1688 | 1.02 (0.83, 1.26)
14 | 1848 | 773 | 2.39 (1.93, 2.96) | 926 | 742 | 1.25 (1.01, 1.54)
18C | 4460 | 1395 | 3.20 (2.53, 4.04) | 1805 | 1355 | 1.33 (1.06, 1.68)
19A | 1415 | 611 | 2.31 (1.91, 2.81) | 618 | 600 | 1.03 (0.85, 1.25)
19F | 655 | 301 | 2.17 (1.76, 2.68) | 287 | 290 | 0.99 (0.80, 1.22)
23F | 1559 | 325 | 4.80 (3.65, 6.32) | 549 | 328 | 1.68 (1.27, 2.22)
Additional Serotypes
8 | 867 | 508 | 1.71 (1.38, 2.12) | 487 | 502 | 0.97 (0.78, 1.20)
10A | 4157 | 2570 | 1.62 (1.31, 2.00) | 2520 | 2437 | 1.03 (0.84, 1.28)
11A | 7169 | 5420 | 1.32 (1.04, 1.68) | 6417 | 5249 | 1.22 (0.96, 1.56)
12F | 5875 | 3075 | 1.91 (1.51, 2.41) | 3445 | 3105 | 1.11 (0.88, 1.39)
15B | 4601 | 3019 | 1.52 (1.13, 2.05) | 3356 | 2874 | 1.17 (0.88, 1.56)
22F | 7568 | 4482 | 1.69 (1.30, 2.20) | 3808 | 4228 | 0.90 (0.69, 1.17)
33F | 7977 | 5693 | 1.40 (1.10, 1.79) | 5571 | 5445 | 1.02 (0.81, 1.30)
Abbreviations: CI = confidence interval; GMT = geometric mean titer; LLOQ = lower limit of quantitation; N = number of participants; OPA = opsonophagocytic activity; PPSV23 = pneumococcal polysaccharide vaccine 23-valent vaccine.

Immunogenicity of Prevnar 20 in Individuals Previously Vaccinated With Pneumococcal Vaccine

A randomized, open-label clinical trial (Study 6) described immune responses to Prevnar 20 in individuals 65 years of age and older previously vaccinated with PPSV23 (≥1 to ≤5 years prior to enrollment), previously vaccinated with Prevnar 13 (≥6 months prior to enrollment), or previously vaccinated with Prevnar 13 followed by PPSV23 (with PPSV23 vaccination ≥1 year prior to enrollment). Participants in this clinical trial previously vaccinated with Prevnar 13 (Prevnar 13 only or followed by PPSV23) were enrolled at sites in the United States and participants previously vaccinated with PPSV23 only were also enrolled from Swedish sites (35.5% in that category). Immune responses elicited by Prevnar 20 were measured by an OPA assay.

OPA GMTs in participants who received PPSV23 1 to 5 years prior to Prevnar 20 were diminished compared to OPA GMTs in participants who received Prevnar 13 at least 6 months previously and compared to OPA GMTs in participants who received Prevnar 13 followed by PPSV23, with the last PPSV23 dose given at least 1 year prior to Prevnar 20.

14.4 Concomitant Vaccine Administration

Individuals 6 Weeks Through 15 Months of Age

In Study 8, the concomitant administration of Pediarix and Hiberix with each of the 3 infant doses of either Prevnar 20 or Prevnar 13 were evaluated 1 month after the third dose. Concomitant administration of single doses of M-M-R II and VARIVAX with the fourth dose of either Prevnar 20 or Prevnar 13 were evaluated 1 month following vaccination. There was no evidence that Prevnar 20, as compared to Prevnar 13, interfered with the antibody responses to these concomitantly administered vaccines.

Individuals 65 Years of Age and Older

Clinical Trial in Individuals to Assess Prevnar 20 Given With Influenza Vaccine, Adjuvanted (Fluad Quadrivalent)

Study 7 was a double-blind, randomized study conducted in individuals 65 years of age and older who had no history of prior pneumococcal vaccination or who had previously received PPSV23 and/or Prevnar 13 at least 6 months prior to enrollment. Study participants were randomized in a 1:1 ratio to receive Prevnar 20 concomitantly administered with Fluad Quadrivalent followed approximately one month later by placebo (Group 1, N=898) or Fluad Quadrivalent concomitantly administered with placebo followed approximately one month later by Prevnar 20 (Group 2, N=898). Pneumococcal serotype-specific OPA GMTs were evaluated 1 month after Prevnar 20 and influenza vaccine strain hemagglutinin inhibition assay (HAI) GMTs were evaluated 1 month after Fluad Quadrivalent. The noninferiority criteria for the comparisons of OPA GMTs (lower limit of the 2- sided 95% CI of the GMT ratio [Group 1/Group 2] >0.5, 2-fold noninferiority criterion) were met for all 20 pneumococcal serotypes in Prevnar 20. The noninferiority criteria for the comparisons of HAI GMTs (lower limit of the 2- sided 95% CI for the GMT ratio [Group 1/Group 2] >0.67, 1.5-fold noninferiority criterion) were also met for all 4 influenza vaccine strains.

16 HOW SUPPLIED/STORAGE AND HANDLING

Product: 50090-6026

NDC: 50090-6026-1 .5 mL in a SYRINGE / 10 in a CARTON

17 PATIENT COUNSELING INFORMATION

Prior to administration of this vaccine, inform the individual of the following:

- The potential benefits and risks of immunization with Prevnar 20 [see Warnings and Precautions (5), Adverse Reactions (6)].
- Any suspected adverse reactions should be reported to their healthcare professional.

This product's labeling may have been updated. For the most recent prescribing information, please visit www.pfizer.com.

US Govt. License No. 3

LAB-1436-3.0

CPT Code 90677